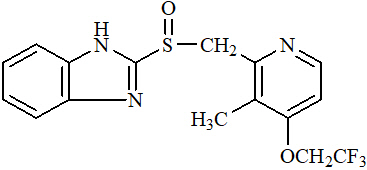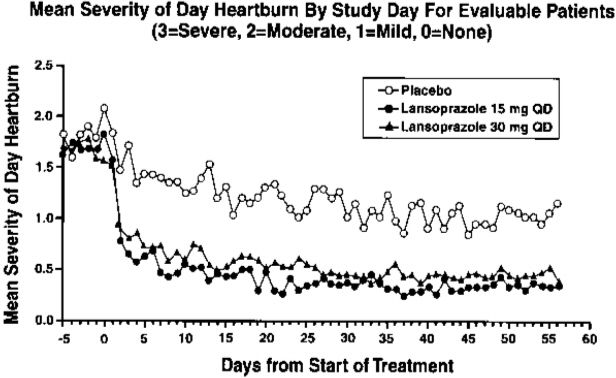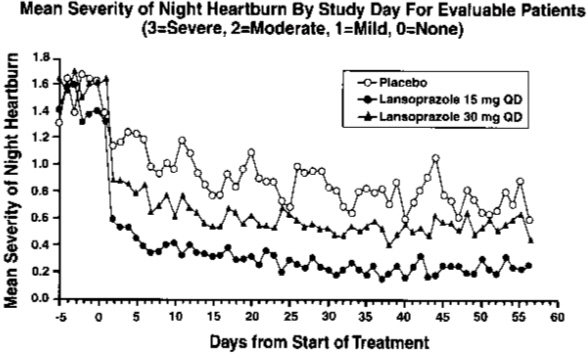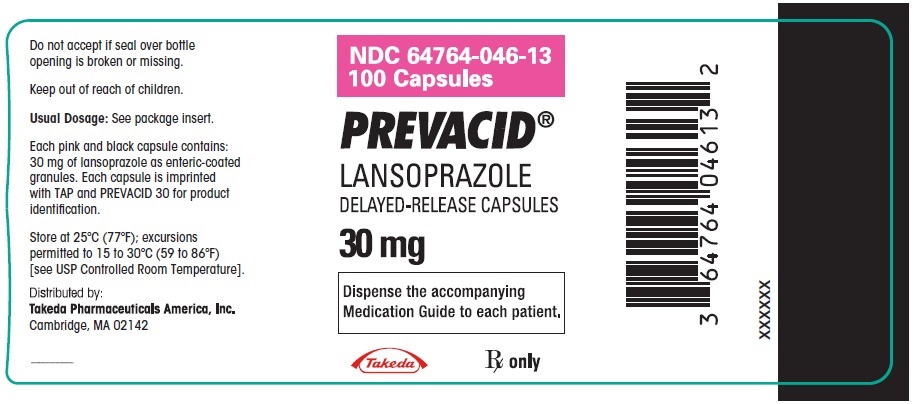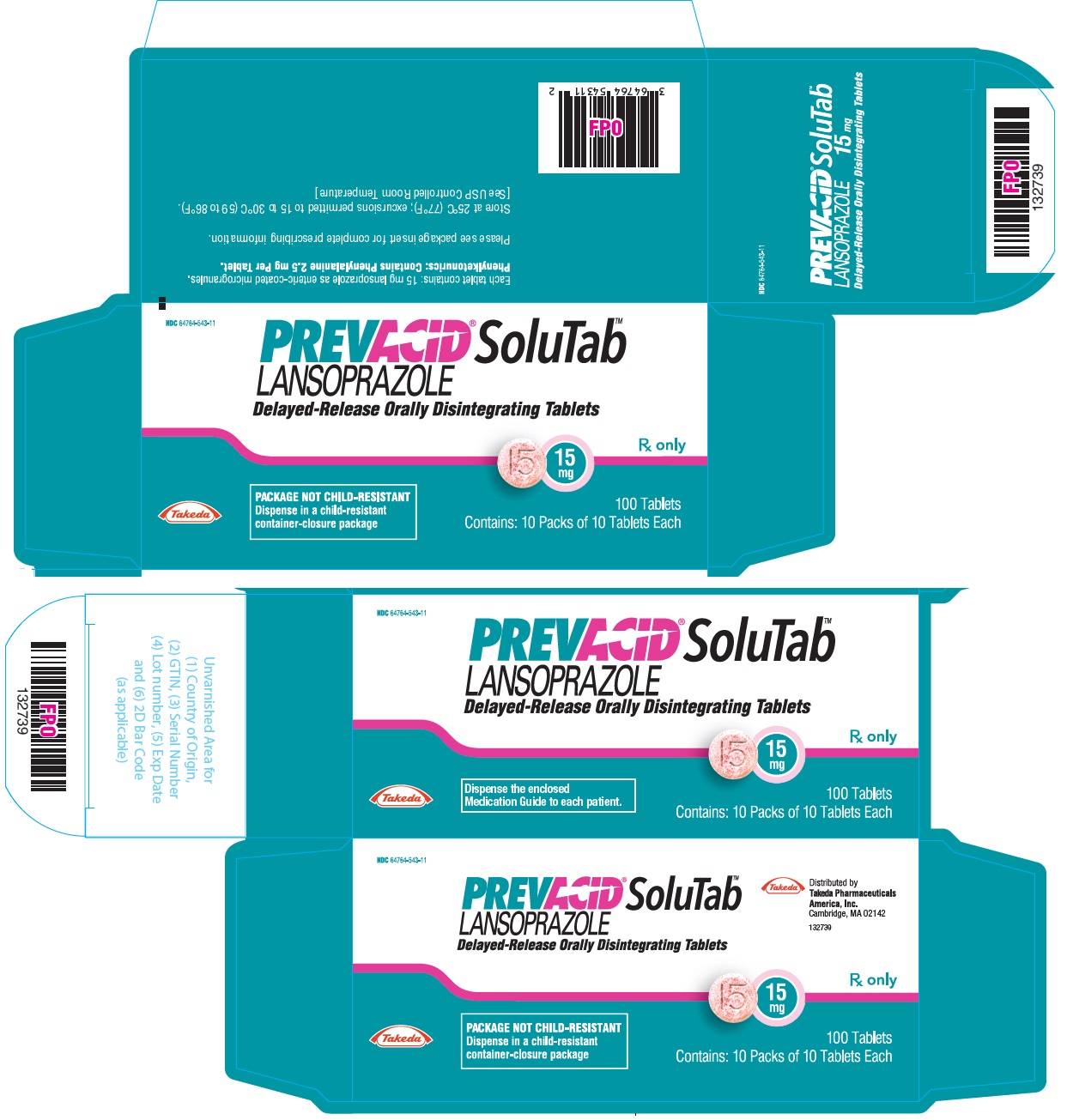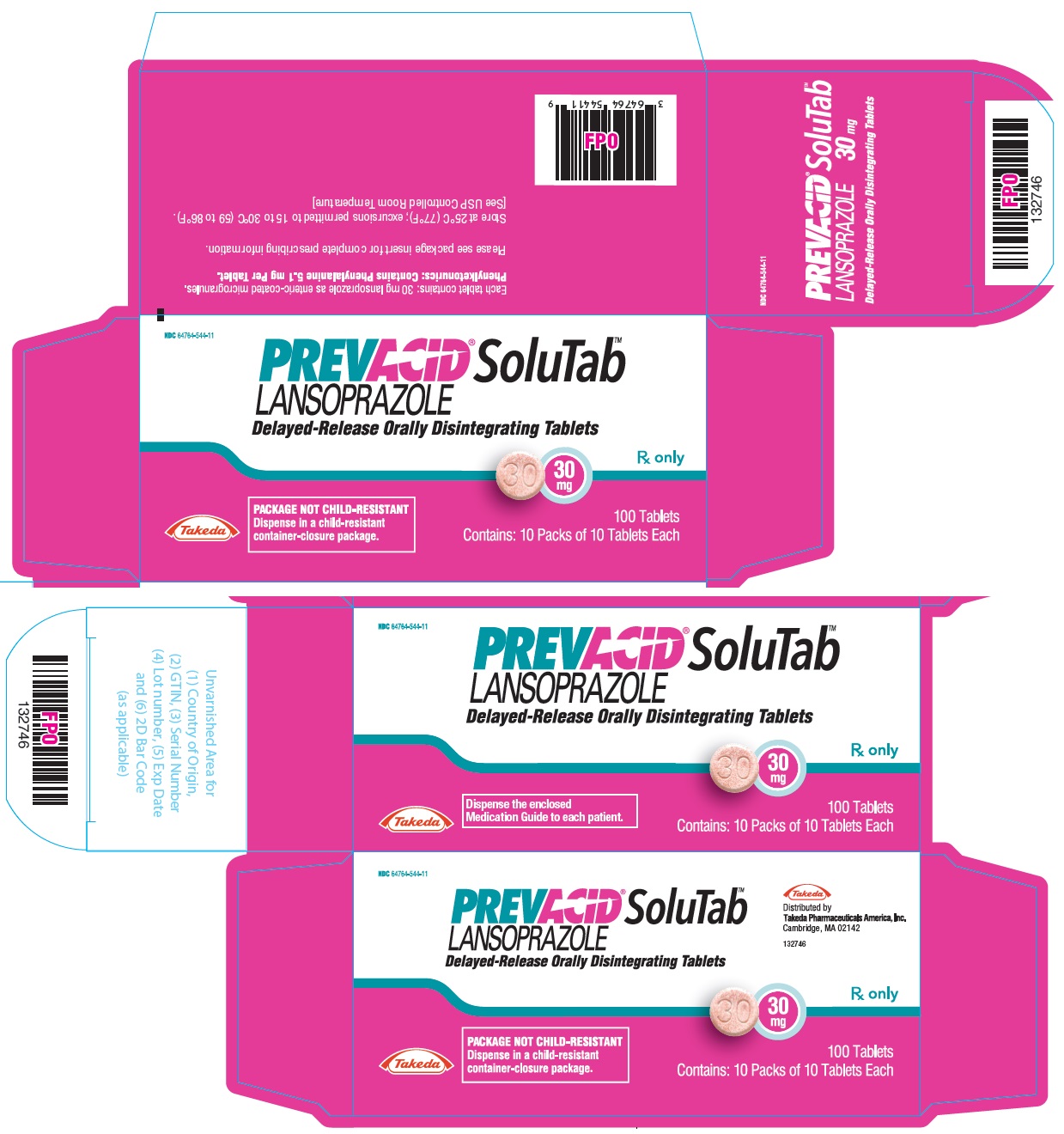 DRUG LABEL: Prevacid
NDC: 64764-046 | Form: CAPSULE, DELAYED RELEASE
Manufacturer: Takeda Pharmaceuticals America, Inc.
Category: prescription | Type: HUMAN PRESCRIPTION DRUG LABEL
Date: 20250708

ACTIVE INGREDIENTS: lansoprazole 30 mg/1 1
INACTIVE INGREDIENTS: sucrose; METHACRYLIC ACID AND ETHYL ACRYLATE COPOLYMER; low-substituted hydroxypropyl cellulose, unspecified; starch, corn; magnesium carbonate; talc; polyethylene glycol, unspecified; titanium dioxide; polysorbate 80; hydroxypropyl cellulose (1600000 wamw); silicon dioxide; D&C Red No. 28; FD&C Blue No. 1; FD&C Red No. 40

HIGHLIGHTS OF PRESCRIBING INFORMATION

These highlights do not include all the information needed to use PREVACID and PREVACID SOLUTAB safely and effectively. See full prescribing information for PREVACID and PREVACID SOLUTAB.
PREVACID (lansoprazole) delayed-release capsules, for oral use PREVACID SOLUTAB (lansoprazole) delayed-release orally disintegrating tablets
Initial U.S. Approval: 1995

1 INDICATIONS AND USAGE

PREVACID and PREVACID SoluTab are proton pump inhibitors (PPIs) indicated for the:

- Treatment of active duodenal ulcer in adults. (1.1)
- Eradication of H. pylori to reduce the risk of duodenal ulcer recurrence in adults. (1.2)
- Maintenance of healed duodenal ulcers in adults. (1.3)
- Treatment of active benign gastric ulcer in adults. (1.4)
- Healing of nonsteroidal anti-inflammatory drugs (NSAID)-associated gastric ulcer in adults. (1.5)
- Risk reduction of NSAID-associated gastric ulcer in adults. (1.6)
- Treatment of symptomatic gastroesophageal reflux disease (GERD) in adults and pediatric patients 1 year of age and older. (1.7)
- Treatment of erosive esophagitis (EE) in adults and pediatric patients 1 year of age and older. (1.8)
- Maintenance of healing of EE in adults. (1.9)
- Pathological hypersecretory conditions, including Zollinger-Ellison syndrome (ZES) in adults. (1.10)

2 DOSAGE AND ADMINISTRATION

Recommended Dosage:

- See full prescribing information for complete dosing information for PREVACID and PREVACID SoluTab by indication and age group and dosage adjustment in patients with severe hepatic impairment. (2.1, 2.2, 2.3)

Administration Instructions (2.4)

PREVACID capsules

- Should be swallowed whole.
- See full prescribing information for alternative administration options.

PREVACID SoluTab

- Should not be broken or cut.
- Should not be chewed.
- Place the tablet on the tongue and allow it to disintegrate, with or without water, until the particles can be swallowed.
- See full prescribing information for alternative administration options.

3 DOSAGE FORMS AND STRENGTHS

- Delayed-release capsules: 30 mg. (3)
- Delayed-release orally disintegrating tablets: 15 mg and 30 mg. (3)

4 CONTRAINDICATIONS

- Contraindicated in patients with known hypersensitivity to any component of the PREVACID or PREVACID SoluTab formulations. (4)
- Patients receiving rilpivirine-containing products. (4, 7)

5 WARNINGS AND PRECAUTIONS

- Gastric Malignancy: In adults, symptomatic response with PREVACID or PREVACID SoluTab does not preclude the presence of gastric malignancy. Consider additional follow-up and diagnostic testing. (5.1)
- Acute Tubulointerstitial Nephritis: Discontinue treatment and evaluate patients. (5.2)
- Clostridium difficile-Associated Diarrhea: PPI therapy may be associated with increased risk of Clostridium difficile-associated diarrhea. (5.3)
- Bone Fracture: Long-term and multiple daily dose PPI therapy may be associated with an increased risk for osteoporosis-related fractures of the hip, wrist or spine. (5.4)
- Severe Cutaneous Adverse Reactions: Discontinue at the first signs or symptoms of severe cutaneous adverse reactions or other signs of hypersensitivity and consider further evaluation. (5.5)
- Cutaneous and Systemic Lupus Erythematosus: Mostly cutaneous; new onset or exacerbation of existing disease; discontinue PREVACID and PREVACID SoluTab and refer to specialist for evaluation. (5.6)
- Cyanocobalamin (Vitamin B12) Deficiency: Daily long-term use (e.g., longer than 3 years) may lead to malabsorption or a deficiency of cyanocobalamin. (5.7)
- Hypomagnesemia and Mineral Metabolism: Hypomagnesemia has been reported rarely with prolonged treatment with PPIs. (5.8)
- Interactions with Investigations for Neuroendocrine Tumors: Increases in intragastric pH may result in hypergastrinemia and enterochromaffin-like cell hyperplasia and increased chromogranin A levels which may interfere with diagnostic investigations for neuroendocrine tumors. (5.9, 7)
- Interaction with Methotrexate: Concomitant use with PPIs may elevate and/or prolong serum concentrations of methotrexate and/or its metabolite, possibly leading to toxicity. With high-dose methotrexate administration, consider a temporary withdrawal of PREVACID. (5.10, 7)
- Patients with Phenylketonuria: Each 15 mg PREVACID SoluTab contains 2.5 mg and each 30 mg PREVACID SoluTab contains 5.1 mg of phenylalanine. (5.11)
- Fundic Gland Polyps: Risk increases with long-term use, especially beyond 1 year. Use the shortest duration of therapy. (5.12)
- Risk of Heart Valve Thickening in Pediatric Patients Less than One Year of Age: PREVACID is not recommended in pediatric patients less than 1 year of age. (5.13, 8.4)

6 ADVERSE REACTIONS

Most commonly reported adverse reactions (≥1%): diarrhea, abdominal pain, nausea and constipation. (6)

To report SUSPECTED ADVERSE REACTIONS, contact Takeda Pharmaceuticals America, Inc. at 1-877-TAKEDA-7 (1-877-825-3327) or FDA at 1-800-FDA-1088 or www.fda.gov/medwatch.

7 DRUG INTERACTIONS

See full prescribing information for a list of clinically important drug interactions. (7)

8 USE IN SPECIFIC POPULATIONS

- Pregnancy: Based on animal data, may cause adverse effects on fetal bone growth and development. (8.1)
- Pediatrics: Use is not recommended for the treatment of symptomatic GERD in patients 1 month to less than 1 year of age; efficacy was not demonstrated and nonclinical studies have demonstrated adverse effects in juvenile rats. (5.13, 8.4)

FULL PRESCRIBING INFORMATION

1 INDICATIONS AND USAGE

1.1 Treatment of Active Duodenal Ulcer

PREVACID and PREVACID SoluTab are indicated in adults for short-term treatment (for four weeks) for healing and symptom relief of active duodenal ulcer [see Clinical Studies (14.1)].

1.2 Eradication of H. pylori to Reduce the Risk of Duodenal Ulcer Recurrence

Triple Therapy: PREVACID or PREVACID SoluTab/amoxicillin/clarithromycin

PREVACID or PREVACID SoluTab in combination with amoxicillin plus clarithromycin as triple therapy is indicated in adults for the treatment of patients with H. pylori infection and duodenal ulcer disease (active or one year history of a duodenal ulcer) to eradicate H. pylori. Eradication of H. pylori has been shown to reduce the risk of duodenal ulcer recurrence [see Clinical Studies (14.2)].

Please refer to the full prescribing information for amoxicillin and clarithromycin.

Dual Therapy: PREVACID or PREVACID SoluTab/amoxicillin

PREVACID or PREVACID SoluTab in combination with amoxicillin as dual therapy is indicated in adults for the treatment of patients with H. pylori infection and duodenal ulcer disease (active or one year history of a duodenal ulcer) who are either allergic or intolerant to clarithromycin or in whom resistance to clarithromycin is known or suspected (see the clarithromycin prescribing information, Microbiology section). Eradication of H. pylori has been shown to reduce the risk of duodenal ulcer recurrence [see Clinical Studies (14.2)].

Please refer to the full prescribing information for amoxicillin.

1.3 Maintenance of Healed Duodenal Ulcers

PREVACID and PREVACID SoluTab are indicated in adults to maintain healing of duodenal ulcers. Controlled studies do not extend beyond 12 months [see Clinical Studies (14.3)].

1.4 Treatment of Active Benign Gastric Ulcer

PREVACID and PREVACID SoluTab are indicated in adults for short-term treatment (up to eight weeks) for healing and symptom relief of active benign gastric ulcer [see Clinical Studies (14.4)].

1.5 Healing of NSAID-Associated Gastric Ulcer

PREVACID and PREVACID SoluTab are indicated in adults for the treatment of NSAID-associated gastric ulcer in patients who continue NSAID use. Controlled studies did not extend beyond eight weeks [see Clinical Studies (14.5)].

1.6 Risk Reduction of NSAID-Associated Gastric Ulcer

PREVACID and PREVACID SoluTab are indicated in adults for reducing the risk of NSAID-associated gastric ulcers in patients with a history of a documented gastric ulcer who require the use of an NSAID. Controlled studies did not extend beyond 12 weeks [see Clinical Studies (14.6)].

1.7 Treatment of Symptomatic Gastroesophageal Reflux Disease (GERD)

PREVACID and PREVACID SoluTab are indicated for short-term treatment in adults and pediatric patients 12 to 17 years of age (up to eight weeks) and pediatric patients one to 11 years of age (up to 12 weeks) for the treatment of heartburn and other symptoms associated with GERD [see Clinical Studies (14.7)].

1.8 Treatment of Erosive Esophagitis (EE)

PREVACID and PREVACID SoluTab are indicated for short-term treatment in adults and pediatric patients 12 to 17 years of age (up to eight weeks) and pediatric patients one to 11 years of age (up to 12 weeks) for healing and symptom relief of all grades of EE.

For adults who do not heal with PREVACID or PREVACID SoluTab for eight weeks (5 to 10%), it may be helpful to give an additional eight weeks of treatment. If there is a recurrence of erosive esophagitis an additional eight week course of PREVACID or PREVACID SoluTab may be considered [see Clinical Studies (14.8)].

1.9 Maintenance of Healing of EE

PREVACID and PREVACID SoluTab are indicated in adults to maintain healing of EE. Controlled studies did not extend beyond 12 months [see Clinical Studies (14.9)].

1.10 Pathological Hypersecretory Conditions Including Zollinger-Ellison Syndrome (ZES)

PREVACID and PREVACID SoluTab are indicated in adults for the long-term treatment of pathological hypersecretory conditions, including Zollinger-Ellison syndrome [see Clinical Studies (14.10)].

2 DOSAGE AND ADMINISTRATION

2.1 Recommended Adult Dosage by Indication

Indication | Recommended Dose | Frequency
Duodenal Ulcers
Short-Term Treatment | 15 mg | Once daily for 4 weeks
Maintenance of Healed | 15 mg | Once daily
Eradication of H. pylori to Reduce the Risk of Duodenal Ulcer Recurrence [Please refer to the amoxicillin and clarithromycin full prescribing information, Contraindications and Warnings and Precautions sections, and for information regarding dosing in elderly and renally-impaired patients.]
Triple Therapy:
PREVACID or PREVACID SoluTab | 30 mg | Twice daily for 10 or 14 days
Amoxicillin | 1 gram | Twice daily for 10 or 14 days
Clarithromycin | 500 mg | Twice daily for 10 or 14 days
Dual Therapy:
PREVACID or PREVACID SoluTab | 30 mg | Three times daily for 14 days
Amoxicillin | 1 gram | Three times daily for 14 days
Benign Gastric Ulcer
Short-Term Treatment | 30 mg | Once daily for up to 8 weeks
NSAID-Associated Gastric Ulcer
Healing | 30 mg | Once daily for 8 weeks [Controlled studies did not extend beyond indicated duration.]
Risk Reduction | 15 mg | Once daily for up to 12 weeks
Gastroesophageal Reflux Disease (GERD)
Short-Term Treatment of Symptomatic GERD | 15 mg | Once daily for up to 8 weeks
Short-Term Treatment of Erosive Esophagitis | 30 mg | Once daily for up to 8 weeks [For patients who do not heal with PREVACID or PREVACID SoluTab for eight weeks (5 to 10%), it may be helpful to give an additional eight weeks of treatment. If there is a recurrence of erosive esophagitis, an additional eight week course of PREVACID or PREVACID SoluTab may be considered.]
Maintenance of Healing of Erosive Esophagitis | 15 mg | Once daily [Controlled studies did not extend beyond 12 months.]
Pathological Hypersecretory Conditions Including Zollinger-Ellison Syndrome | 60 mg | Once daily [Varies with individual patient. Recommended adult starting dose is 60 mg once daily. Doses should be adjusted to individual patient needs and should continue for as long as clinically indicated. Dosages up to 90 mg twice daily have been administered. Daily dose of greater than 120 mg should be administered in divided doses. Some patients with Zollinger-Ellison syndrome have been treated continuously with PREVACID for more than four years.]

2.2 Recommended Pediatric Dosage by Indication

Pediatric Patients 1 to 11 Years of Age

In clinical studies, PREVACID was not administered beyond 12 weeks in 1 to 11 year olds. It is not known if PREVACID is safe and effective if used longer than the recommended duration. Do not exceed the recommended dose and duration of use in pediatric patients as outlined below [see Use in Specific Populations (8.4)].

Indication | Recommended Dose | Frequency
Short-Term Treatment of Symptomatic GERD and Short-Term Treatment of Erosive Esophagitis
≤30 kg | 15 mg | Once daily for up to 12 weeks
>30 kg | 30 mg | Once daily for up to 12 weeks

Pediatric Patients 12 to 17 Years of Age

Indication | Recommended Dose | Frequency
Short-Term Treatment of Symptomatic GERD
Non-erosive GERD | 15 mg | Once daily for up to 8 weeks
Erosive Esophagitis | 30 mg | Once daily for up to 8 weeks

2.3 Hepatic Impairment

The recommended dosage is 15 mg orally daily in patients with severe liver impairment (Child-Pugh C) [see Use in Specific Populations (8.6)].

2.4 Important Administration Information

- Take PREVACID or PREVACID SoluTab before meals.
- Do not crush or chew PREVACID capsule or PREVACID SoluTab.
- Take PREVACID or PREVACID SoluTab at least 30 minutes prior to sucralfate [see Drug Interactions (7)].
- Antacids may be used concomitantly with PREVACID or PREVACID SoluTab.
- Missed doses: If a dose is missed, administer as soon as possible. However, if the next scheduled dose is due, do not take the missed dose, and take the next dose on time. Do not take two doses at one time to make up for a missed dose.

PREVACID capsules

- Swallow whole; do not chew.
- For patients who have difficulty swallowing capsules, PREVACID capsules can be opened and administered orally or via a nasogastric tube in the soft foods or liquids specified below.
- Administration of PREVACID in foods or liquids other than those discussed below have not been studied clinically and therefore are not recommended.
  Administration in Soft Foods (applesauce, ENSURE pudding, cottage cheese, yogurt or strained pears):
  1. Open capsule.
  2. Sprinkle intact granules on one tablespoon of either applesauce, ENSURE pudding, cottage cheese, yogurt or strained pears.
  3. Swallow immediately.
  Administration in Liquids (apple juice, orange juice or tomato juice):
  1. Open capsule.
  2. Sprinkle intact granules into a small volume of either apple juice, orange juice or tomato juice (60 mL – approximately two ounces).
  3. Mix briefly.
  4. Swallow immediately.
  5. To ensure complete delivery of the dose, rinse the glass with two or more volumes of juice and swallow the contents immediately.
  Administration with Apple Juice Through a Nasogastric Tube (≥16 French)
  1. Open capsule.
  2. Sprinkle intact granules into 40 mL of apple juice.
  3. Mix briefly.
  4. Using a catheter-tipped syringe, draw up the mixture.
  5. Inject through the nasogastric tube into the stomach.
  6. Flush with additional apple juice to clear the tube.

PREVACID SoluTab

- Do not break or cut.
- Place the tablet on the tongue, allow it to disintegrate, with or without water, until the microgranules can be swallowed. Do not chew the microgranules.
- The tablet typically disintegrates in less than one minute.
- Alternatively, for children or other patients who have difficulty swallowing tablets, PREVACID SoluTab can be administered with water via oral syringe or NG tube as follows:
  Administration with Water in an Oral Syringe
  1. Place a 15 mg tablet in oral syringe and draw up 4 mL of water, or place a 30 mg tablet in oral syringe and draw up 10 mL of water.
  2. Shake gently to allow for a quick dispersal.
  3. After the tablet has dispersed, administer the contents within 15 minutes of mixing into the mouth. Do not save the water and microgranule mixture for later use.
  4. Refill the syringe with approximately 2 mL (5 mL for the 30 mg tablet) of water, shake gently, and administer any remaining contents.
  Administration with Water via a NG Tube (≥8 French)
  1. Place a 15 mg tablet in a catheter-tip syringe and draw up 4 mL of water, or place a 30 mg tablet in a catheter-tip syringe and draw up 10 mL of water.
  2. Shake gently to allow for a quick dispersal.
  3. After the tablet has dispersed, shake the catheter-tip syringe gently in order to keep the microgranules from settling, and immediately inject the mixture through the NG tube into the stomach within 15 minutes of mixing. Do not save the water and microgranule mixture for later use.
  4. Refill the catheter-tip syringe with approximately 5 mL of water, shake gently, and flush the tube.

3 DOSAGE FORMS AND STRENGTHS

PREVACID delayed-release capsules:

- 15 mg strength is not currently marketed by Takeda Pharmaceuticals America, Inc.
- 30 mg strength is an opaque, pink and black capsule imprinted with "TAP" and "PREVACID 30".

PREVACID SoluTab delayed-release orally disintegrating tablets:

- 15 mg strength is a white to yellowish white, uncoated round tablet containing orange to dark brown speckles with "15" debossed on one side.
- 30 mg strength is a white to yellowish white, uncoated round tablet containing orange to dark brown speckles with "30" debossed on one side.

4 CONTRAINDICATIONS

- PREVACID and PREVACID SoluTab are contraindicated in patients with known hypersensitivity to any component of the formulation. Hypersensitivity reactions may include anaphylaxis, anaphylactic shock, angioedema, bronchospasm, acute tubulointerstitial nephritis, and urticaria [see Warnings and Precautions (5.2), Adverse Reactions (6)].
- Proton Pump Inhibitors (PPIs), including PREVACID and PREVACID SoluTab, are contraindicated with rilpivirine-containing products [see Drug Interactions (7)].
- For information about contraindications of antibacterial agents (clarithromycin and amoxicillin) indicated in combination with PREVACID or PREVACID SoluTab, refer to the Contraindications section of their prescribing information.

5 WARNINGS AND PRECAUTIONS

5.1 Presence of Gastric Malignancy

In adults, symptomatic response to therapy with PREVACID or PREVACID SoluTab does not preclude the presence of gastric malignancy. Consider additional follow-up and diagnostic testing in adult patients who have a suboptimal response or an early symptomatic relapse after completing treatment with a PPI. In older patients, also consider an endoscopy.

5.2 Acute Tubulointerstitial Nephritis

Acute tubulointerstial nephritis (TIN) has been observed in patients taking PPIs and may occur at any point during PPI therapy. Patients may present with varying signs and symptoms from symptomatic hypersensitivity reactions to non-specific symptoms of decreased renal function (e.g., malaise, nausea, anorexia). In reported case series, some patients were diagnosed on biopsy and in the absence of extra-renal manifestations (e.g., fever, rash or arthralgia).

Discontinue PREVACID or PREVACID SoluTab and evaluate patients with suspected acute TIN [see Contraindications (4)].

5.3 Clostridium difficile-Associated Diarrhea

Published observational studies suggest that PPI therapy like PREVACID and PREVACID SoluTab may be associated with an increased risk of Clostridium difficile-associated diarrhea (CDAD), especially in hospitalized patients. This diagnosis should be considered for diarrhea that does not improve [see Adverse Reactions (6.2)].

Patients should use the lowest dose and shortest duration of PPI therapy appropriate to the condition being treated.

CDAD has been reported with use of nearly all antibacterial agents. For more information specific to antibacterial agents (clarithromycin and amoxicillin) indicated for use in combination with PREVACID or PREVACID SoluTab, refer to Warnings and Precautions section of their prescribing information.

5.4 Bone Fracture

Several published observational studies suggest that PPI therapy may be associated with an increased risk for osteoporosis-related fractures of the hip, wrist or spine. The risk of fracture was increased in patients who received high-dose, defined as multiple daily doses, and long-term PPI therapy (a year or longer). Patients should use the lowest dose and shortest duration of PPI therapy appropriate to the condition being treated. Patients at risk for osteoporosis-related fractures should be managed according to established treatment guidelines [see Dosage and Administration (2), Adverse Reactions (6.2)].

5.5 Severe Cutaneous Adverse Reactions

Severe cutaneous adverse reactions, including Stevens-Johnson syndrome (SJS) and toxic epidermal necrolysis (TEN), drug reaction with eosinophilia and systemic symptoms (DRESS), and acute generalized exanthematous pustulosis (AGEP) have been reported in association with the use of PPIs [see Adverse Reactions (6.2)]. Discontinue PREVACID or PREVACID SoluTab at the first signs or symptoms of severe cutaneous adverse reactions or other signs of hypersensitivity and consider further evaluation.

5.6 Cutaneous and Systemic Lupus Erythematosus

Cutaneous lupus erythematosus (CLE) and systemic lupus erythematosus (SLE) have been reported in patients taking PPIs, including lansoprazole. These events have occurred as both new onset and an exacerbation of existing autoimmune disease. The majority of PPI-induced lupus erythematosus cases were CLE.

The most common form of CLE reported in patients treated with PPIs was subacute CLE (SCLE) and occurred within weeks to years after continuous drug therapy in patients ranging from infants to the elderly. Generally, histological findings were observed without organ involvement.

Systemic lupus erythematosus (SLE) is less commonly reported than CLE in patients receiving PPIs. PPI-associated SLE is usually milder than nondrug induced SLE. Onset of SLE typically occurred within days to years after initiating treatment primarily in patients ranging from young adults to the elderly. The majority of patients presented with rash; however, arthralgia and cytopenia were also reported.

Avoid administration of PPIs for longer than medically indicated. If signs or symptoms consistent with CLE or SLE are noted in patients receiving PREVACID or PREVACID SoluTab, discontinue the drug and refer the patient to the appropriate specialist for evaluation. Most patients improve with discontinuation of the PPI alone in four to 12 weeks. Serological testing (e.g., ANA) may be positive and elevated serological test results may take longer to resolve than clinical manifestations.

5.7 Cyanocobalamin (Vitamin B12) Deficiency

Daily treatment with any acid-suppressing medications over a long period of time (e.g., longer than three years) may lead to malabsorption of cyanocobalamin (Vitamin B12) caused by hypo- or achlorhydria. Rare reports of cyanocobalamin deficiency occurring with acid-suppressing therapy have been reported in the literature. This diagnosis should be considered if clinical symptoms consistent with cyanocobalamin deficiency are observed in patients treated with PREVACID or PREVACID SoluTab.

5.8 Hypomagnesemia and Mineral Metabolism

Hypomagnesemia, symptomatic and asymptomatic, has been reported rarely in patients treated with PPIs for at least three months, in most cases after a year of therapy. Serious adverse events include tetany, arrhythmias, and seizures. Hypomagnesemia may lead to hypocalcemia and/or hypokalemia and may exacerbate underlying hypocalcemia in at-risk patients. In most patients, treatment of hypomagnesemia required magnesium replacement and discontinuation of the PPI.

For patients expected to be on prolonged treatment or who take PPIs with medications such as digoxin or drugs that may cause hypomagnesemia (e.g., diuretics), health care professionals may consider monitoring magnesium levels prior to initiation of PPI treatment and periodically [see Adverse Reactions (6.2)].

Consider monitoring magnesium and calcium levels prior to initiation of PREVACID or PREVACID SoluTab and periodically while on treatment in patients with a preexisting risk of hypocalcemia (e.g., hypoparathyroidism). Supplement with magnesium and/or calcium, as necessary. If hypocalcemia is refractory to treatment, consider discontinuing the PPI.

5.9 Interactions with Investigations for Neuroendocrine Tumors

Serum chromogranin A (CgA) levels increase secondary to drug-induced decreases in gastric acidity. The increased CgA level may cause false positive results in diagnostic investigations for neuroendocrine tumors. Healthcare providers should temporarily stop lansoprazole treatment at least 14 days before assessing CgA levels and consider repeating the test if initial CgA levels are high. If serial tests are performed (e.g., for monitoring), the same commercial laboratory should be used for testing, as reference ranges between tests may vary [see Drug Interactions (7), Clinical Pharmacology (12.2)].

5.10 Interaction with Methotrexate

Literature suggests that concomitant use of PPIs with methotrexate (primarily at high dose) may elevate and prolong serum levels of methotrexate and/or its metabolite, possibly leading to methotrexate toxicities. In high-dose methotrexate administration, a temporary withdrawal of the PPI may be considered in some patients [see Drug Interactions (7), Clinical Pharmacology (12.3)].

5.11 Patients with Phenylketonuria

Phenylalanine can be harmful to patients with phenylketonuria (PKU). PREVACID SoluTab contains phenylalanine, a component of aspartame. Each 15 mg tablet contains 2.5 mg and each 30 mg tablet contains 5.1 mg of phenylalanine. Before prescribing PREVACID SoluTab to a patient with PKU, consider the combined daily amount of phenylalanine from all sources, including PREVACID SoluTab.

5.12 Fundic Gland Polyps

PPI use is associated with an increased risk of fundic gland polyps that increases with long-term use, especially beyond one year. Most PPI users who developed fundic gland polyps were asymptomatic and fundic gland polyps were identified incidentally on endoscopy. Use the shortest duration of PPI therapy appropriate to the condition being treated.

5.13 Risk of Heart Valve Thickening in Pediatric Patients Less Than One Year of Age

PREVACID and PREVACID SoluTab are not approved in pediatric patients less than one year of age. Nonclinical studies in juvenile rats with lansoprazole have demonstrated an adverse effect of heart valve thickening. The risk of heart valve injury does not appear to be relevant to patients one year of age and older [see Use in Specific Populations (8.4)].

6 ADVERSE REACTIONS

The following serious adverse reactions are described below and elsewhere in labeling:

- Acute Tubulointerstitial Nephritis [see Warnings and Precautions (5.2)]
- Clostridium difficile-Associated Diarrhea [see Warnings and Precautions (5.3)]
- Bone Fracture [see Warnings and Precautions (5.4)]
- Severe Cutaneous Adverse Reactions [see Warnings and Precautions (5.5)]
- Cutaneous and Systemic Lupus Erythematosus [see Warnings and Precautions (5.6)]
- Cyanocobalamin (Vitamin B12) Deficiency [see Warnings and Precautions (5.7)]
- Hypomagnesemia and Mineral Metabolism [see Warnings and Precautions (5.8)]
- Fundic Gland Polyps [see Warnings and Precautions (5.12)]

6.1 Clinical Trials Experience

Because clinical trials are conducted under widely varying conditions, adverse reaction rates observed in the clinical trials of a drug cannot be directly compared to rates in the clinical trials of another drug and may not reflect the rates observed in clinical practice.

Worldwide, over 10,000 patients have been treated with PREVACID in Phase 2 or Phase 3 clinical trials involving various dosages and durations of treatment. In general, PREVACID treatment has been well-tolerated in both short-term and long-term trials.

The following adverse reactions were reported by the treating physician to have a possible or probable relationship to drug in 1% or more of PREVACID-treated patients and occurred at a greater rate in PREVACID-treated patients than placebo-treated patients in Table 1.

Table 1. Incidence of Possibly or Probably Treatment-Related Adverse Reactions in Short-Term, Placebo-Controlled PREVACID Studies
Body System/Adverse Reaction | PREVACID (N=2768) % | Placebo (N=1023) %
Body as a Whole
Abdominal Pain | 2.1 | 1.2
Digestive System
Constipation | 1.0 | 0.4
Diarrhea | 3.8 | 2.3
Nausea | 1.3 | 1.2

Headache was also seen at greater than 1% incidence but was more common on placebo. The incidence of diarrhea was similar between patients who received placebo and patients who received 15 and 30 mg of PREVACID, but higher in the patients who received 60 mg of PREVACID (2.9, 1.4, 4.2, and 7.4%, respectively).

The most commonly reported possibly or probably treatment-related adverse event during maintenance therapy was diarrhea.

In the risk reduction study of PREVACID for NSAID-associated gastric ulcers, the incidence of diarrhea for patients treated with PREVACID, misoprostol, and placebo was 5, 22, and 3%, respectively.

Another study for the same indication, where patients took either a COX-2 inhibitor or lansoprazole and naproxen, demonstrated that the safety profile was similar to the prior study. Additional reactions from this study not previously observed in other clinical trials with PREVACID included contusion, duodenitis, epigastric discomfort, esophageal disorder, fatigue, hunger, hiatal hernia, hoarseness, impaired gastric emptying, metaplasia, and renal impairment.

Additional adverse experiences occurring in less than 1% of patients or subjects who received PREVACID in domestic trials are shown below:

Body as a Whole – abdomen enlarged, allergic reaction, asthenia, back pain, candidiasis, carcinoma, chest pain (not otherwise specified), chills, edema, fever, flu syndrome, halitosis, infection (not otherwise specified), malaise, neck pain, neck rigidity, pain, pelvic pain

Cardiovascular System – angina, arrhythmia, bradycardia, cerebrovascular accident/cerebral infarction, hypertension/hypotension, migraine, myocardial infarction, palpitations, shock (circulatory failure), syncope, tachycardia, vasodilation

Digestive System – abnormal stools, anorexia, bezoar, cardiospasm, cholelithiasis, colitis, dry mouth, dyspepsia, dysphagia, enteritis, eructation, esophageal stenosis, esophageal ulcer, esophagitis, fecal discoloration, flatulence, gastric nodules/fundic gland polyps, gastritis, gastroenteritis, gastrointestinal anomaly, gastrointestinal disorder, gastrointestinal hemorrhage, glossitis, gum hemorrhage, hematemesis, increased appetite, increased salivation, melena, mouth ulceration, nausea and vomiting, nausea and vomiting and diarrhea, gastrointestinal moniliasis, rectal disorder, rectal hemorrhage, stomatitis, tenesmus, thirst, tongue disorder, ulcerative colitis, ulcerative stomatitis

Endocrine System – diabetes mellitus, goiter, hypothyroidism

Hemic and Lymphatic System – anemia, hemolysis, lymphadenopathy

Metabolism and Nutritional Disorders – avitaminosis, gout, dehydration, hyperglycemia/hypoglycemia, peripheral edema, weight gain/loss

Musculoskeletal System – arthralgia, arthritis, bone disorder, joint disorder, leg cramps, musculoskeletal pain, myalgia, myasthenia, ptosis, synovitis

Nervous System – abnormal dreams, agitation, amnesia, anxiety, apathy, confusion, convulsion, dementia, depersonalization, depression, diplopia, dizziness, emotional lability, hallucinations, hemiplegia, hostility aggravated, hyperkinesia, hypertonia, hypesthesia, insomnia, libido decreased/increased, nervousness, neurosis, paresthesia, sleep disorder, somnolence, thinking abnormality, tremor, vertigo

Respiratory System – asthma, bronchitis, cough increased, dyspnea, epistaxis, hemoptysis, hiccup, laryngeal neoplasia, lung fibrosis, pharyngitis, pleural disorder, pneumonia, respiratory disorder, upper respiratory inflammation/infection, rhinitis, sinusitis, stridor

Skin and Appendages – acne, alopecia, contact dermatitis, dry skin, fixed eruption, hair disorder, maculopapular rash, nail disorder, pruritus, rash, skin carcinoma, skin disorder, sweating, urticaria

Special Senses – abnormal vision, amblyopia, blepharitis, blurred vision, cataract, conjunctivitis, deafness, dry eyes, ear/eye disorder, eye pain, glaucoma, otitis media, parosmia, photophobia, retinal degeneration/disorder, taste loss, taste perversion, tinnitus, visual field defect

Urogenital System – abnormal menses, breast enlargement, breast pain, breast tenderness, dysmenorrhea, dysuria, gynecomastia, impotence, kidney calculus, kidney pain, leukorrhea, menorrhagia, menstrual disorder, penis disorder, polyuria, testis disorder, urethral pain, urinary frequency, urinary retention, urinary tract infection, urinary urgency, urination impaired, vaginitis

6.2 Postmarketing Experience

Additional adverse experiences have been reported since PREVACID and PREVACID SoluTab have been marketed. The majority of these cases are foreign-sourced and a relationship to PREVACID or PREVACID SoluTab has not been established. Because these reactions were reported voluntarily from a population of unknown size, estimates of frequency cannot be made. These events are listed below by COSTART body system.

Body as a Whole – anaphylactic/anaphylactoid reactions, systemic lupus erythematosus; Digestive System – hepatotoxicity, pancreatitis, vomiting; Hemic and Lymphatic System – agranulocytosis, aplastic anemia, hemolytic anemia, leukopenia, neutropenia, pancytopenia, thrombocytopenia, and thrombotic thrombocytopenic purpura; Infections and Infestations – Clostridium difficile-associated diarrhea; Metabolism and Nutritional Disorders – hypomagnesemia, hypocalcemia, hypokalemia, hyponatremia; Musculoskeletal System – bone fracture, myositis; Skin and Appendages – severe dermatologic reactions including erythema multiforme, SJS/TEN (some fatal), DRESS, AGEP, cutaneous lupus erythematosus; Special Senses – speech disorder; Urogenital System – interstitial nephritis, urinary retention.

6.3 Combination Therapy with Amoxicillin and Clarithromycin

In clinical trials using combination therapy with PREVACID plus amoxicillin and clarithromycin, and PREVACID plus amoxicillin, no adverse reactions peculiar to these drug combinations were observed. Adverse reactions that have occurred have been limited to those that had been previously reported with PREVACID, amoxicillin, or clarithromycin.

Triple Therapy: PREVACID/amoxicillin/clarithromycin

The most frequently reported adverse reactions for patients who received triple therapy for 14 days were diarrhea (7%), headache (6%), and taste perversion (5%). There were no statistically significant differences in the frequency of reported adverse reactions between the 10 and 14 day triple therapy regimens. No treatment-emergent adverse reactions were observed at significantly higher rates with triple therapy than with any dual therapy regimen.

Dual Therapy: PREVACID/amoxicillin

The most frequently reported adverse reactions for patients who received PREVACID three times daily plus amoxicillin three times daily dual therapy were diarrhea (8%) and headache (7%). No treatment-emergent adverse reactions were observed at significantly higher rates with PREVACID three times daily plus amoxicillin three times daily dual therapy than with PREVACID alone.

For information about adverse reactions with antibacterial agents (amoxicillin and clarithromycin) indicated in combination with PREVACID or PREVACID SoluTab, refer to the Adverse Reactions section of their prescribing information.

6.4 Laboratory Values

The following changes in laboratory parameters in patients who received PREVACID were reported as adverse reactions:

Abnormal liver function tests, increased SGOT (AST), increased SGPT (ALT), increased creatinine, increased alkaline phosphatase, increased globulins, increased GGTP, increased/decreased/abnormal WBC, abnormal AG ratio, abnormal RBC, bilirubinemia, blood potassium increased, blood urea increased, crystal urine present, eosinophilia, hemoglobin decreased, hyperlipemia, increased/decreased electrolytes, increased/decreased cholesterol, increased glucocorticoids, increased LDH, increased/decreased/abnormal platelets, increased gastrin levels and positive fecal occult blood. Urine abnormalities such as albuminuria, glycosuria, and hematuria were also reported. Additional isolated laboratory abnormalities were reported.

In the placebo-controlled studies, when SGOT (AST) and SGPT (ALT) were evaluated, 0.4% (4/978) and 0.4% (11/2677) patients, who received placebo and PREVACID, respectively, had enzyme elevations greater than three times the upper limit of normal range at the final treatment visit. None of these patients who received PREVACID reported jaundice at any time during the study.

In clinical trials using combination therapy with PREVACID plus amoxicillin and clarithromycin, and PREVACID plus amoxicillin, no increased laboratory abnormalities particular to these drug combinations were observed.

For information about laboratory value changes with antibacterial agents (amoxicillin and clarithromycin) indicated in combination with PREVACID or PREVACID SoluTab, refer to the Adverse Reactions section of their prescribing information.

7 DRUG INTERACTIONS

Tables 2 and 3 include drugs with clinically important drug interactions and interaction with diagnostics when administered concomitantly with PREVACID or PREVACID SoluTab and instructions for preventing or managing them.

Consult the labeling of concomitantly used drugs to obtain further information about interactions with PPIs.

Table 2. Clinically Relevant Interactions Affecting Drugs Coadministered with PREVACID or PREVACID SoluTab and Interactions with Diagnostics
Antiretrovirals
Clinical Impact: | The effect of PPIs on antiretroviral drugs is variable. The clinical importance and the mechanisms behind these interactions are not always known.; - Decreased exposure of some antiretroviral drugs (e.g., rilpivirine, atazanavir, and nelfinavir) when used concomitantly with lansoprazole may reduce antiviral effect and promote the development of drug resistance. - Increased exposure of other antiretroviral drugs (e.g., saquinavir) when used concomitantly with lansoprazole may increase toxicity of the antiretroviral drugs. - There are other antiretroviral drugs which do not result in clinically relevant interactions with lansoprazole.
Intervention: | Rilpivirine-containing products: Concomitant use with PREVACID or PREVACID SoluTab is contraindicated [see Contraindications (4)]. See prescribing information. Atazanavir: See prescribing information for atazanavir for dosing information. Nelfinavir: Avoid concomitant use with PREVACID or PREVACID SoluTab. See prescribing information for nelfinavir. Saquinavir: See the prescribing information for saquinavir and monitor for potential saquinavir toxicities. Other antiretrovirals: See prescribing information.
Warfarin
Clinical Impact: | Increased INR and prothrombin time in patients receiving PPIs and warfarin concomitantly. Increases in INR and prothrombin time may lead to abnormal bleeding and even death.
Intervention: | Monitor INR and prothrombin time. Dose adjustment of warfarin may be needed to maintain target INR range. See prescribing information for warfarin.
Methotrexate
Clinical Impact: | Concomitant use of PPIs with methotrexate (primarily at high dose) may elevate and prolong serum concentrations of methotrexate and/or its metabolite hydroxymethotrexate, possibly leading to methotrexate toxicities. No formal drug interaction studies of high-dose methotrexate with PPIs have been conducted [see Warnings and Precautions (5.10)].
Intervention: | A temporary withdrawal of PREVACID or PREVACID SoluTab may be considered in some patients receiving high-dose methotrexate.
Digoxin
Clinical Impact: | Potential for increased exposure of digoxin.
Intervention: | Monitor digoxin concentrations. Dose adjustment of digoxin may be needed to maintain therapeutic drug concentrations. See prescribing information for digoxin.
Theophylline
Clinical Impact: | Increased clearance of theophylline [see Clinical Pharmacology (12.3)].
Intervention: | Individual patients may require additional titration of their theophylline dosage when PREVACID or PREVACID SoluTab is started or stopped to ensure clinically effective blood concentrations.
Drugs Dependent on Gastric pH for Absorption (e.g., iron salts, erlotinib, dasatinib, nilotinib, mycophenolate mofetil, ketoconazole/itraconazole)
Clinical Impact: | Lansoprazole can reduce the absorption of other drugs due to its effect on reducing intragastric acidity.
Intervention: | Mycophenolate mofetil (MMF): Coadministration of PPIs in healthy subjects and in transplant patients receiving MMF has been reported to reduce the exposure to the active metabolite, mycophenolic acid (MPA), possibly due to a decrease in MMF solubility at an increased gastric pH. The clinical relevance of reduced MPA exposure on organ rejection has not been established in transplant patients receiving PREVACID and MMF. Use PREVACID and PREVACID SoluTab with caution in transplant patients receiving MMF. See the prescribing information for other drugs dependent on gastric pH for absorption.
Combination Therapy with Clarithromycin and Amoxicillin
Clinical Impact: | Concomitant administration of clarithromycin with other drugs can lead to serious adverse reactions, including potentially fatal arrhythmias, and are contraindicated. Amoxicillin also has drug interactions.
Intervention: | - See Contraindications and Warnings and Precautions in prescribing information for clarithromycin. - See Drug Interactions in prescribing information for amoxicillin.
Tacrolimus
Clinical Impact: | Potentially increased exposure of tacrolimus, especially in transplant patients who are intermediate or poor metabolizers of CYP2C19.
Intervention: | Monitor tacrolimus whole blood trough concentrations. Dose adjustment of tacrolimus may be needed to maintain therapeutic drug concentrations. See prescribing information for tacrolimus.
Interactions with Investigations of Neuroendocrine Tumors
Clinical Impact: | CgA levels increase secondary to PPI-induced decreases in gastric acidity. The increased CgA level may cause false positive results in diagnostic investigations for neuroendocrine tumors [see Warnings and Precautions (5.9), Clinical Pharmacology (12.2)].
Intervention: | Temporarily stop PREVACID or PREVACID SoluTab treatment at least 14 days before assessing CgA levels and consider repeating the test if initial CgA levels are high. If serial tests are performed (e.g., for monitoring), the same commercial laboratory should be used for testing, as reference ranges between tests may vary.
Interaction with Secretin Stimulation Test
Clinical Impact: | Hyper-response in gastrin secretion in response to secretin stimulation test, falsely suggesting gastrinoma.
Intervention: | Temporarily stop PREVACID or PREVACID SoluTab treatment at least 28 days before assessing to allow gastrin levels to return to baseline [see Clinical Pharmacology (12.2)].
False Positive Urine Tests for THC
Clinical Impact: | There have been reports of false positive urine screening tests for tetrahydrocannabinol (THC) in patients receiving PPIs.
Intervention: | An alternative confirmatory method should be considered to verify positive results.

Table 3. Clinically Relevant Interactions Affecting PREVACID or PREVACID SoluTab When Coadministered with Other Drugs
CYP2C19 OR CYP3A4 Inducers
Clinical Impact: | Decreased exposure of lansoprazole when used concomitantly with strong inducers [see Clinical Pharmacology (12.3)].
Intervention: | St John's Wort, rifampin: Avoid concomitant use with PREVACID or PREVACID SoluTab. Ritonavir-containing products: See prescribing information.
CYP2C19 or CYP3A4 Inhibitors
Clinical Impact: | Increased exposure of lansoprazole is expected when used concomitantly with strong inhibitors [see Clinical Pharmacology (12.3)].
Intervention: | Voriconazole: See prescribing information.
Sucralfate
Clinical Impact: | Decreased and delayed absorption of lansoprazole [see Clinical Pharmacology (12.3)].
Intervention: | Take PREVACID or PREVACID SoluTab at least 30 minutes prior to sucralfate [see Dosage and Administration (2.4)].

8 USE IN SPECIFIC POPULATIONS

8.1 Pregnancy

Risk Summary

Available data from published observational studies overall do not indicate an association of adverse pregnancy outcomes with lansoprazole treatment (see Data).

In animal reproduction studies, oral administration of lansoprazole to rats during organogenesis through lactation at 6.4 times the maximum recommended human dose produced reductions in the offspring in femur weight, femur length, crown-rump length and growth plate thickness (males only) on postnatal Day 21 (see Data). These effects were associated with reduction in body weight gain. Advise pregnant women of the potential risk to the fetus.

The estimated background risk of major birth defects and miscarriage for the indicated populations are unknown. All pregnancies have a background risk of birth defect, loss, or other adverse outcomes. In the US general population, the estimated background risk of major birth defects and miscarriage in clinically recognized pregnancies is 2 to 4% and 15 to 20%, respectively.

If PREVACID or PREVACID SoluTab is administered with clarithromycin, the pregnancy information for clarithromycin also applies to the combination regimen. Refer to the prescribing information for clarithromycin for more information on use in pregnancy.

Data

Human Data

Available data from published observational studies failed to demonstrate an association of adverse pregnancy-related outcomes and lansoprazole use. Methodological limitations of these observational studies cannot definitely establish or exclude any drug-associated risk during pregnancy. In a prospective study by the European Network of Teratology Information Services, outcomes from a group of 62 pregnant women administered median daily doses of 30 mg of lansoprazole were compared to a control group of 868 pregnant women who did not take any PPIs. There was no difference in the rate of major malformations between women exposed to PPIs and the control group, corresponding to a Relative Risk (RR)=1.04, [95% Confidence Interval (CI) 0.25-4.21]. In a population-based retrospective cohort study covering all live births in Denmark from 1996 to 2008, there was no significant increase in major birth defects during analysis of first trimester exposure to lansoprazole in 794 live births. A meta-analysis that compared 1,530 pregnant women exposed to PPIs in at least the first trimester with 133,410 unexposed pregnant women showed no significant increases in risk for congenital malformations or spontaneous abortion with exposure to PPIs (for major malformations Odds Ratio (OR)=1.12, [95% CI 0.86-1.45] and for spontaneous abortions OR=1.29, [95% CI 0.84-1.97]).

Animal Data

No adverse effects on embryo-fetal development occurred in studies performed in pregnant rats at oral lansoprazole doses up to 150 mg/kg/day (40 times the recommended human dose [30 mg/day] based on body surface area) administered during organogenesis and pregnant rabbits at oral lansoprazole doses up to 30 mg/kg/day (16 times the recommended human dose based on body surface area) administered during organogenesis.

A pre- and postnatal developmental toxicity study in rats with additional endpoints to evaluate bone development was performed with lansoprazole at oral doses of 10 to 100 mg/kg/day (0.7 to 6.4 times the maximum recommended human lansoprazole dose of 30 mg based on AUC [area under the plasma concentration-time curve]) administered during organogenesis through lactation. Maternal effects observed at 100 mg/kg/day (6.4 times the maximum recommended human lansoprazole dose of 30 mg based on AUC) included increased gestation period, decreased body weight gain during gestation, and decreased food consumption. The number of stillbirths was increased at this dose, which may have been secondary to maternal toxicity. Body weight of pups was reduced at 100 mg/kg/day starting on postnatal Day 11. Femur weight, femur length, and crown-rump length were reduced at 100 mg/kg/day on postnatal Day 21. Femur weight was still decreased in the 100 mg/kg/day group at age 17 to 18 weeks. Growth plate thickness was decreased in the 100 mg/kg/day males on postnatal Day 21, and was increased in the 30 and 100 mg/kg/day males at age 17 to 18 weeks. The effects on bone parameters were associated with reduction in body weight gain.

8.2 Lactation

Risk Summary

There is no information regarding the presence of lansoprazole in human milk, the effects on the breastfed infant, or the effects on milk production. However, lansoprazole and its metabolites are present in rat milk. The developmental and health benefits of breastfeeding should be considered along with the mother's clinical need for PREVACID or PREVACID SoluTab and any potential adverse effects on the breastfed child from PREVACID or PREVACID SoluTab or from the underlying maternal condition.

8.4 Pediatric Use

The safety and effectiveness of PREVACID and PREVACID SoluTab have been established in pediatric patients one year to 17 years of age for short-term treatment of symptomatic GERD and erosive esophagitis.

In clinical studies of symptomatic GERD and erosive esophagitis, PREVACID was not administered beyond 12 weeks in patients one year to 11 years of age. It is not known if PREVACID and PREVACID SoluTab are safe and effective if used longer than the recommended duration. Do not exceed the recommended dose and duration of use in pediatric patients (see Juvenile Animal Toxicity Data).

PREVACID was not effective in pediatric patients with symptomatic GERD one month to less than one year of age in a multicenter, double-blind, placebo - controlled study. Therefore, safety and effectiveness have not been established in patients less than one year of age. Nonclinical studies in juvenile rats have demonstrated an adverse effect of heart valve thickening and bone changes at lansoprazole doses higher than the maximum recommended equivalent human dose.

Neonate to less than one year of age

The pharmacokinetics of lansoprazole were studied in pediatric patients with GERD aged less than 28 days and one to 11 months. Compared to healthy adults receiving 30 mg, neonates had higher exposure (mean weight-based normalized AUC values 2.04 and 1.88 fold higher at doses of 0.5 and 1 mg/kg/day, respectively). Infants aged ≤10 weeks had clearance and exposure values that were similar to neonates. Infants aged greater than 10 weeks who received 1 mg/kg/day had mean AUC values that were similar to adults who received a 30 mg dose.

Lansoprazole was not found to be effective in a US and Polish four week, multicenter, double-blind, placebo-controlled, parallel-group study of 162 patients between one month and less than 12 months of age with symptomatic GERD based on a medical history of crying/fussing/irritability associated with feedings who had not responded to conservative GERD management (i.e., nonpharmacologic intervention) for seven to 14 days. Patients received lansoprazole as a suspension daily (0.2 to 0.3 mg/kg/day in infants ≤10 weeks of age or 1.0 to 1.5 mg/kg/day in infants greater than 10 weeks or placebo) for up to four weeks of double-blind treatment.

The primary efficacy endpoint was assessed by greater than 50% reduction from baseline in either the percent of feedings with a crying/fussing/irritability episode or the duration (minutes) of a crying/fussing/irritability episode within one hour after feeding.

There was no difference in the percentage of responders between the lansoprazole pediatric suspension group and placebo group (54% in both groups).

There were no adverse events reported in pediatric clinical studies (one month to less than 12 months of age) that were not previously observed in adults.

Based on the results of the Phase 3 efficacy study, lansoprazole was not shown to be effective. Therefore, these results do not support the use of lansoprazole in treating symptomatic GERD in infants.

One year to 11 years of age

In an uncontrolled, open-label, US multicenter study, 66 pediatric patients (one year to 11 years of age) with GERD were assigned, based on body weight, to receive an initial dose of either PREVACID 15 mg daily if ≤30 kg or PREVACID 30 mg daily if greater than 30 kg administered for eight to 12 weeks. The PREVACID dose was increased (up to 30 mg twice daily) in 24 of 66 pediatric patients after two or more weeks of treatment if they remained symptomatic. At baseline, 85% of patients had mild to moderate overall GERD symptoms (assessed by investigator interview), 58% had non-erosive GERD and 42% had erosive esophagitis (assessed by endoscopy).

After eight to 12 weeks of PREVACID treatment, the intent-to-treat analysis demonstrated an approximate 50% reduction in frequency and severity of GERD symptoms.

Twenty-one of 27 erosive esophagitis patients were healed at eight weeks and 100% of patients were healed at 12 weeks by endoscopy (Table 4).

Table 4. GERD Symptom Improvement and Erosive Esophagitis Healing Rates in Pediatric Patients Age 1 Year to 11 Years of Age
GERD | Final Visit [At Week 8 or Week 12] % (n/N)
Symptomatic GERD
Improvement in Overall GERD Symptoms [Symptoms assessed by patients diary kept by caregiver.] | 76% (47/62 [No data were available for four pediatric patients.])
Erosive Esophagitis
Improvement in Overall GERD Symptoms | 81% (22/27)
Healing Rate | 100% (27/27)

In a study of 66 pediatric patients in the age group one year to 11 years old after treatment with PREVACID given orally in doses of 15 mg daily to 30 mg twice daily, increases in serum gastrin levels were similar to those observed in adult studies. Median fasting serum gastrin levels increased 89% from 51 pg/mL at baseline to 97 pg/mL [interquartile range (25th to 75th percentile) of 71 to 130 pg/mL] at the final visit.

The pediatric safety of PREVACID capsules has been assessed in 66 pediatric patients aged one to 11 years of age. Of the 66 patients with GERD, 85% (56/66) took PREVACID for eight weeks and 15% (10/66) took it for 12 weeks.

The most frequently reported (two or more patients) treatment-related adverse reactions in patients one to 11 years of age (N=66) were constipation (5%) and headache (3%).

Twelve years to 17 years of age

In an uncontrolled, open-label, US multicenter study, 87 adolescent patients (12 years to 17 years of age) with symptomatic GERD were treated with PREVACID for eight to 12 weeks. Baseline upper endoscopies classified these patients into two groups: 64 (74%) non-erosive GERD and 23 (26%) erosive esophagitis (EE). The non-erosive GERD patients received PREVACID 15 mg daily for eight weeks and the EE patients received PREVACID 30 mg daily for eight to 12 weeks. At baseline, 89% of these patients had mild to moderate overall GERD symptoms (assessed by investigator interviews). During eight weeks of PREVACID treatment, adolescent patients experienced a 63% reduction in frequency and a 69% reduction in severity of GERD symptoms based on diary results.

Twenty-one of 22 (95.5%) adolescent erosive esophagitis patients were healed after eight weeks of PREVACID treatment. One patient remained unhealed after 12 weeks of treatment (Table 5).

Table 5. GERD Symptom Improvement and Erosive Esophagitis Healing Rates in Pediatric Patients Age 12 Years to 17 Years of Age
GERD | Final Visit % (n/N)
Symptomatic GERD (All Patients)
Improvement in Overall GERD Symptoms [Symptoms assessed by patient diary (parents/caregivers as necessary).] | 73.2% (60/82) [No data available for five patients.]
Non-erosive GERD
Improvement in Overall GERD Symptoms | 71.2% (42/59)
Erosive Esophagitis
Improvement in Overall GERD Symptoms | 78.3% (18/23)
Healing Rate [Data from one healed patient was excluded from this analysis due to timing of final endoscopy.] | 95.5% (21/22)

In these 87 adolescent patients, increases in serum gastrin levels were similar to those observed in adult studies, median fasting serum gastrin levels increased 42% from 45 pg/mL at baseline to 64 pg/mL [interquartile range (25th to 75th percentile) of 44 to 88 pg/mL] at the final visit. (Normal serum gastrin levels are 25 to 111 pg/mL.)

The safety of PREVACID capsules has been assessed in these 87 adolescent patients. Of the 87 adolescent patients with GERD, 6% (5/87) took PREVACID for less than six weeks, 93% (81/87) for six to 10 weeks, and 1% (1/87) for greater than 10 weeks.

The most frequently reported (at least 3%) treatment-related adverse reactions in these patients were headache (7%), abdominal pain (5%), nausea (3%) and dizziness (3%). Treatment-related dizziness, reported in this prescribing information as occurring in less than 1% of adult patients, was reported in this study by three adolescent patients with non-erosive GERD, who had dizziness concurrently with other reactions (such as migraine, dyspnea, and vomiting).

Juvenile Animal Toxicity Data

Heart Valve Thickening

In two oral toxicity studies, thickening of the mitral heart valve occurred in juvenile rats treated with lansoprazole. Heart valve thickening was observed primarily with oral dosing initiated on postnatal Day 7 (age equivalent to neonatal humans) and postnatal Day 14 (human age equivalent of approximately one year) at doses of 250 mg/kg/day and higher (at postnatal Day 7 and postnatal Day 14, respectively 6.2 times and 4.2 times the daily pediatric dose of 15 mg in pediatric patients age one to 11 years weighing 30 kg or less, based on AUC). The treatment durations associated with heart valve thickening ranged from 5 days to 8 weeks. The findings reversed or trended towards reversibility after a 4-week drug-free recovery period. The incidence of heart valve thickening after initiation of dosing on postnatal Day 21 (human age equivalent of approximately two years) was limited to a single rat (1/24) in groups given 500 mg/kg/day for 4 or 8 weeks (approximately 5.2 times the daily pediatric dose of 15 mg in pediatric patients age one to 11 years weighing 30 kg or less, based on AUC). Based on exposure margins, the risk of heart valve injury does not appear to be relevant to patients one year of age and older.

Bone Changes

In an eight-week oral toxicity study in juvenile rats with dosing initiated on postnatal Day 7, doses equal to or greater than 100 mg/kg/day (2.5 times the daily pediatric dose of 15 mg in children age one to 11 years weighing 30 kg or less, based on AUC) produced delayed growth, with impairment of weight gain observed as early as postnatal Day 10 (age equivalent to neonatal humans). At the end of treatment, the signs of impaired growth at 100 mg/kg/day and higher included reductions in body weight (14 to 44% compared to controls), absolute weight of multiple organs, femur weight, femur length, and crown-rump length. Femoral growth plate thickness was reduced only in males and only at the 500 mg/kg/day dose. The effects related to delayed growth persisted through the end of the four-week recovery period. Longer term data were not collected.

8.5 Geriatric Use

Of the total number of patients (n=21,486) in clinical studies of PREVACID, 16% of patients were aged 65 years and over, while 4% were 75 years and over. No overall differences in safety or effectiveness were observed between these patients and younger patients and other reported clinical experience has not identified significant differences in responses between geriatric and younger patients, but greater sensitivity of some older individuals cannot be ruled out [see Clinical Pharmacology (12.3)].

8.6 Hepatic Impairment

In patients with various degrees of chronic hepatic impairment the exposure to lansoprazole was increased compared to healthy subjects with normal hepatic function [see Clinical Pharmacology (12.3)]. No dosage adjustment for PREVACID or PREVACID SoluTab is necessary for patients with mild (Child-Pugh Class A) or moderate (Child-Pugh Class B) hepatic impairment. The recommended dosage is 15 mg orally daily in patients with severe hepatic impairment (Child-Pugh Class C) [see Dosage and Administration (2.3)].

10 OVERDOSAGE

Lansoprazole is not removed from the circulation by hemodialysis. In one reported overdose, a patient consumed 600 mg of PREVACID with no adverse reaction. Oral lansoprazole doses up to 5000 mg/kg in rats [approximately 1300 times the 30 mg human dose based on body surface area (BSA)] and in mice (about 675.7 times the 30 mg human dose based on BSA) did not produce deaths or any clinical signs.

In the event of over-exposure, treatment should be symptomatic and supportive.

If over-exposure occurs, call your poison control center at 1-800-222-1222 for current information on the management of poisoning or over-exposure.

11 DESCRIPTION

The active ingredient in PREVACID Delayed-Release Capsules and PREVACID SoluTab Delayed-Release Orally Disintegrating Tablets is lansoprazole, a substituted benzimidazole, 2-[[[3-methyl-4-(2,2,2-trifluoroethoxy)-2-pyridyl] methyl] sulfinyl] benzimidazole, a compound that inhibits gastric acid secretion. Its empirical formula is C16H14F3N3O2S with a molecular weight of 369.37. Lansoprazole has the following structure:

Lansoprazole is a white to brownish-white odorless crystalline powder which melts with decomposition at approximately 166°C. Lansoprazole is freely soluble in dimethylformamide; soluble in methanol; sparingly soluble in ethanol; slightly soluble in ethyl acetate, dichloromethane and acetonitrile; very slightly soluble in ether; and practically insoluble in hexane and water.

Lansoprazole is stable when exposed to light for up to two months. The rate of degradation of the compound in aqueous solution increases with decreasing pH. The degradation half-life of the drug substance in aqueous solution at 25°C is approximately 0.5 hour at pH 5.0 and approximately 18 hours at pH 7.0.

PREVACID is supplied in delayed-release capsules and PREVACID SoluTab is supplied in delayed-release orally disintegrating tablets (SoluTab) for oral administration.

PREVACID is available in one dosage strength: 30 mg of lansoprazole per capsule. Each delayed-release capsule contains enteric-coated granules consisting of 30 mg of lansoprazole (active ingredient) and the following inactive ingredients: sugar sphere, sucrose, methacrylic acid copolymer, low substituted hydroxypropyl cellulose, starch, magnesium carbonate, talc, polyethylene glycol, titanium dioxide, polysorbate 80, hydroxypropyl cellulose, colloidal silicon dioxide, D&C Red No. 28, FD&C Blue No. 1, and FD&C Red No. 40. The 15 mg strength of PREVACID is not currently marketed by Takeda Pharmaceuticals America, Inc.

PREVACID SoluTab is available in two dosage strengths: 15 and 30 mg of lansoprazole per tablet. Each delayed-release orally disintegrating tablet contains enteric-coated microgranules consisting of 15 or 30 mg of lansoprazole (active ingredient) and the following inactive ingredients: mannitol, methacrylic acid, hydroxypropyl cellulose, lactose monohydrate-microcrystalline cellulose sphere, triethyl citrate, crospovidone, polyacrylate, magnesium carbonate, aspartame [Phenylketonurics: PREVACID SoluTab Contains Phenylalanine 2.5 mg per 15 mg Tablet and 5.1 mg per 30 mg Tablet.] , glyceryl monostearate, hypromellose, magnesium stearate, citric acid, titanium dioxide, talc, artificial strawberry flavor, polyethylene glycol, polysorbate 80 and ferric oxide.

12 CLINICAL PHARMACOLOGY

12.1 Mechanism of Action

Lansoprazole belongs to a class of antisecretory compounds, the substituted benzimidazoles, that suppress gastric acid secretion by specific inhibition of the (H^+, K^+)-ATPase enzyme system at the secretory surface of the gastric parietal cell. Because this enzyme system is regarded as the acid (proton) pump within the parietal cell, lansoprazole has been characterized as a gastric acid-pump inhibitor, in that it blocks the final step of acid production. This effect is dose-related and leads to inhibition of both basal and stimulated gastric acid secretion irrespective of the stimulus. Lansoprazole does not exhibit anticholinergic or histamine type-2 antagonist activity.

12.2 Pharmacodynamics

Antisecretory Activity

After oral administration, lansoprazole was shown to significantly decrease the basal acid output and significantly increase the mean gastric pH and percent of time the gastric pH was greater than three and greater than four. Lansoprazole also significantly reduced meal-stimulated gastric acid output and secretion volume, as well as pentagastrin-stimulated acid output. In patients with hypersecretion of acid, lansoprazole significantly reduced basal and pentagastrin-stimulated gastric acid secretion. Lansoprazole inhibited the normal increases in secretion volume, acidity and acid output induced by insulin.

The intragastric pH results of a five day, pharmacodynamic, crossover study of 15 and 30 mg of once daily lansoprazole are presented in Table 6:

Table 6. Mean Antisecretory Effects After Single and Multiple Daily PREVACID Dosing
 |  | PREVACID
Parameter | Baseline Value | 15 mg |  | 30 mg
Parameter | Baseline Value | Day 1 | Day 5 | Day 1 | Day 5
Mean 24 Hour pH | 2.1 | 2.7 [(p<0.05) vs baseline only.] | 4.0 | 3.6 [(p<0.05) vs baseline and lansoprazole 15 mg.] | 4.9
Mean Nighttime pH | 1.9 | 2.4 | 3.0 | 2.6 | 3.8
% Time Gastric pH>3 | 18 | 33 | 59 | 51 | 72
% Time Gastric pH>4 | 12 | 22 | 49 | 41 | 66
NOTE: An intragastric pH of greater than four reflects a reduction in gastric acid by 99%.

After the initial dose in this study, increased gastric pH was seen within one to two hours with 30 mg of lansoprazole and two to three hours with 15 mg of lansoprazole. After multiple daily dosing, increased gastric pH was seen within the first hour postdosing with 30 mg of lansoprazole and within one to two hours postdosing with 15 mg of lansoprazole.

Acid suppression may enhance the effect of antimicrobials in eradicating Helicobacter pylori (H. pylori). The percentage of time gastric pH was elevated above five and six was evaluated in a crossover study of PREVACID given daily, twice daily and three times daily (Table 7).

Table 7. Mean Antisecretory Effects After Five Days of Twice Daily and Three Times Daily Dosing
 | PREVACID
Parameter | 30 mg daily | 15 mg twice daily | 30 mg twice daily | 30 mg three times daily
% Time Gastric pH>5 | 43 | 47 | 59 [(p<0.05) vs PREVACID 30 mg daily] | 77 [(p<0.05) vs PREVACID 30 mg daily, 15 and 30 mg twice daily.]
% Time Gastric pH>6 | 20 | 23 | 28 | 45

The inhibition of gastric acid secretion as measured by intragastric pH gradually returned to normal over two to four days after multiple doses. There was no indication of rebound gastric acidity.

Enterochromaffin-like (ECL) Cell Effects

During lifetime exposure of rats with up to 150 mg/kg/day of lansoprazole dosed seven days per week, marked hypergastrinemia was observed followed by ECL cell proliferation and formation of carcinoid tumors, especially in female rats. Gastric biopsy specimens from the body of the stomach from approximately 150 patients treated continuously with lansoprazole for at least one year did not show evidence of ECL cell effects similar to those seen in rat studies. Longer term data are needed to rule out the possibility of an increased risk of the development of gastric tumors in patients receiving long-term therapy with lansoprazole [see Nonclinical Toxicology (13.1)].

Other Gastric Effects in Humans

Lansoprazole did not significantly affect mucosal blood flow in the fundus of the stomach. Due to the normal physiologic effect caused by the inhibition of gastric acid secretion, a decrease of about 17% in blood flow in the antrum, pylorus, and duodenal bulb was seen. Lansoprazole significantly slowed the gastric emptying of digestible solids. Lansoprazole increased serum pepsinogen levels and decreased pepsin activity under basal conditions and in response to meal stimulation or insulin injection. As with other agents that elevate intragastric pH, increases in gastric pH were associated with increases in nitrate-reducing bacteria and elevation of nitrite concentration in gastric juice in patients with gastric ulcer. No significant increase in nitrosamine concentrations was observed.

Serum Gastrin Effects

In over 2100 patients, median fasting serum gastrin levels increased 50 to 100% from baseline but remained within normal range after treatment with 15 to 60 mg of oral lansoprazole. These elevations reached a plateau within two months of therapy and returned to pretreatment levels within four weeks after discontinuation of therapy.

Increased gastrin causes enterochromaffin-like cell hyperplasia and increased serum CgA levels. The increased CgA levels may cause false positive results in diagnostic investigations for neuroendocrine tumors [see Warnings and Precautions (5.9)].

Endocrine Effects

Human studies for up to one year have not detected any clinically significant effects on the endocrine system. Hormones studied include testosterone, luteinizing hormone (LH), follicle stimulating hormone (FSH), sex hormone binding globulin (SHBG), dehydroepiandrosterone sulfate (DHEA-S), prolactin, cortisol, estradiol, insulin, aldosterone, parathormone, glucagon, thyroid stimulating hormone (TSH), triiodothyronine (T3), thyroxine (T4), and somatotropic hormone (STH). Lansoprazole in oral doses of 15 to 60 mg for up to one year had no clinically significant effect on sexual function. In addition, lansoprazole in oral doses of 15 to 60 mg for two to eight weeks had no clinically significant effect on thyroid function. In 24 month carcinogenicity studies in Sprague-Dawley rats with daily lansoprazole dosages up to 150 mg/kg, proliferative changes in the Leydig cells of the testes, including benign neoplasm, were increased compared to control rats.

Other Effects

No systemic effects of lansoprazole on the central nervous system, lymphoid, hematopoietic, renal, hepatic, cardiovascular, or respiratory systems have been found in humans. Among 56 patients who had extensive baseline eye evaluations, no visual toxicity was observed after lansoprazole treatment (up to 180 mg/day) for up to 58 months. After lifetime lansoprazole exposure in rats, focal pancreatic atrophy, diffuse lymphoid hyperplasia in the thymus, and spontaneous retinal atrophy were seen.

12.3 Pharmacokinetics

Absorption:

PREVACID and PREVACID SoluTab contain an enteric-coated granule formulation of lansoprazole (because lansoprazole is acid-labile), so that absorption of lansoprazole begins only after the granules leave the stomach. The mean peak plasma levels of lansoprazole occur at approximately 1.7 hours. After a single-dose administration of 15 to 60 mg of oral lansoprazole, the peak plasma concentrations (Cmax) of lansoprazole and the area under the plasma concentration curves (AUCs) of lansoprazole were approximately proportional to the administered dose. Lansoprazole does not accumulate and its pharmacokinetics are unaltered by multiple dosing. The absolute bioavailability is over 80%. In healthy subjects, the mean (±SD) plasma half-life was 1.5 (±1.0) hours. Both the Cmax and AUC are diminished by about 50 to 70% if lansoprazole is given 30 minutes after food, compared to the fasting condition. There is no significant food effect if lansoprazole is given before meals.

Distribution: Lansoprazole is 97% bound to plasma proteins. Plasma protein binding is constant over the concentration range of 0.05 to 5 mcg/mL.

Elimination

Metabolism: Lansoprazole is extensively metabolized in the liver. Two metabolites have been identified in measurable quantities in plasma (the hydroxylated sulfinyl and sulfone derivatives of lansoprazole). These metabolites have very little or no antisecretory activity. Lansoprazole is thought to be transformed into two active species which inhibit acid secretion by blocking the proton pump [(H^+, K^+)-ATPase enzyme system] at the secretory surface of the gastric parietal cell. The two active species are not present in the systemic circulation. The plasma elimination half-life of lansoprazole is less than two hours while the acid inhibitory effect lasts more than 24 hours. Therefore, the plasma elimination half-life of lansoprazole does not reflect its duration of suppression of gastric acid secretion.

Excretion: Following single-dose oral administration of PREVACID, virtually no unchanged lansoprazole was excreted in the urine. In one study, after a single oral dose of ^14C-lansoprazole, approximately one-third of the administered radiation was excreted in the urine and two-thirds was recovered in the feces. This implies a significant biliary excretion of the lansoprazole metabolites.

Specific Populations

Pediatric Patients:

One to 17 years of age

The pharmacokinetics of lansoprazole were studied in pediatric patients with GERD aged one to 11 years and 12 to 17 years in two separate clinical studies. In children aged one to 11 years, lansoprazole was dosed 15 mg daily for subjects weighing ≤30 kg and 30 mg daily for subjects weighing greater than 30 kg. Mean Cmax and AUC values observed on Day 5 of dosing were similar between the two dose groups and were not affected by weight or age within each weight-adjusted dose group used in the study. In adolescent subjects aged 12 to 17 years, subjects were randomized to receive lansoprazole at 15 or 30 mg daily. Mean Cmax and AUC values of lansoprazole were not affected by body weight or age; and nearly dose-proportional increases in mean Cmax and AUC values were observed between the two dose groups in the study. Overall, lansoprazole pharmacokinetics in pediatric patients aged one to 17 years were similar to those observed in healthy adult subjects.

Geriatric Patients:

The clearance of lansoprazole is decreased in the elderly, with elimination half-life increased approximately 50 to 100%. Because the mean half-life in the elderly remains between 1.9 to 2.9 hours, repeated once daily dosing does not result in accumulation of lansoprazole. Peak plasma levels were not increased in the elderly [see Use in Specific Populations (8.5)].

Male and Female Patients:

In a study comparing 12 male and six female human subjects who received lansoprazole, no sex-related differences were found in pharmacokinetics and intragastric pH results.

Racial or Ethnic Groups:

The pooled mean pharmacokinetic parameters of PREVACID from twelve US studies (N=513) were compared to the mean pharmacokinetic parameters from two Asian studies (N=20). The mean AUCs of PREVACID in Asian subjects were approximately twice those seen in pooled US data; however, the inter-individual variability was high. The Cmax values were comparable.

Patients with Renal Impairment:

In patients with severe renal impairment, plasma protein binding decreased by 1 to 1.5% after administration of 60 mg of lansoprazole. Patients with renal impairment had a shortened elimination half-life and decreased total AUC (free and bound). The AUC for free lansoprazole in plasma, however, was not related to the degree of renal impairment; and the Cmax and Tmax (time to reach the maximum concentration) were not different than the Cmax and Tmax from subjects with normal renal function. Therefore, the pharmacokinetics of lansoprazole were not clinically different in patients with mild, moderate or severe renal impairment compared to healthy subjects with normal renal function.

Patients with Hepatic Impairment:

In patients with mild (Child-Pugh Class A) or moderate (Child-Pugh Class B) hepatic impairment there was an approximate 3-fold increase in mean AUC compared to healthy subjects with normal hepatic function following multiple oral doses of 30 mg PREVACID for seven days. The corresponding mean plasma half-life of lansoprazole was prolonged from 1.5 to four hours (Child-Pugh A) or five hours (Child-Pugh B).

In patients with compensated and decompensated cirrhosis, there was an approximate 6- and 5-fold increase in AUC, respectively, compared to healthy subjects with normal hepatic function following a single oral dose of 30 mg PREVACID [see Dosage and Administration (2.3), Use in Specific Populations (8.6)].

Drug Interaction Studies

Effect of Lansoprazole on Other Drugs

Cytochrome P450 Interactions:

Lansoprazole is metabolized through the cytochrome P450 system, specifically through the CYP3A and CYP2C19 isozymes. Studies have shown that PREVACID does not have clinically significant interactions with other drugs metabolized by the cytochrome P450 system, such as warfarin, antipyrine, indomethacin, ibuprofen, phenytoin, propranolol, prednisone, diazepam, or clarithromycin in healthy subjects. These compounds are metabolized through various cytochrome P450 isozymes including CYP1A2, CYP2C9, CYP2C19, CYP2D6, and CYP3A.

Theophylline:

When PREVACID was administered concomitantly with theophylline (CYP1A2, CYP3A), a minor increase (10%) in the clearance of theophylline was seen. Because of the small magnitude and the direction of the effect on theophylline clearance, this interaction is unlikely to be of clinical concern [see Drug Interactions (7)].

Methotrexate and 7-hydroxymethotrexate:

In an open-label, single-arm, eight day, pharmacokinetic study of 28 adult rheumatoid arthritis patients (who required the chronic use of 7.5 to 15 mg of methotrexate given weekly), administration of seven days of naproxen 500 mg twice daily and PREVACID 30 mg daily had no effect on the pharmacokinetics of methotrexate and 7-hydroxymethotrexate. While this study was not designed to assess the safety of this combination of drugs, no major adverse reactions were noted. However, this study was conducted with low doses of methotrexate. A drug interaction study with high doses of methotrexate has not been conducted [see Warnings and Precautions (5.10)].

Amoxicillin:

PREVACID has also been shown to have no clinically significant interaction with amoxicillin.

Sucralfate:

In a single-dose crossover study examining PREVACID 30 mg administered alone and concomitantly with sucralfate 1 gram, absorption of lansoprazole was delayed and the bioavailability was reduced by 17% when administered concomitantly with sucralfate [see Dosage and Administration (2.4), Drug Interactions (7)].

Antacids:

In clinical trials, antacids were administered concomitantly with PREVACID and there was no evidence of a change in the efficacy of PREVACID.

Clopidogrel:

Clopidogrel is metabolized to its active metabolite in part by CYP2C19. A study of healthy subjects who were CYP2C19 extensive metabolizers, receiving once daily administration of clopidogrel 75 mg alone or concomitantly with PREVACID 30 mg (n=40), for nine days was conducted. The mean AUC of the active metabolite of clopidogrel was reduced by approximately 14% (mean AUC ratio was 86%, with 90% CI of 80 to 92%) when PREVACID was coadministered compared to administration of clopidogrel alone.

Pharmacodynamic parameters were also measured and demonstrated that the change in inhibition of platelet aggregation (induced by 5 mcM ADP) was related to the change in the exposure to clopidogrel active metabolite. The effect on exposure to the active metabolite of clopidogrel and on clopidogrel-induced platelet inhibition is not considered clinically important.

Effect of Other Drugs on Lansoprazole

Because lansoprazole is metabolized by CYP2C19 and CYP3A4, inducers and inhibitors of these enzymes may potentially alter exposure of lansoprazole.

12.4 Microbiology

Microbiology

Lansoprazole, clarithromycin and/or amoxicillin have been shown to be active against most strains of Helicobacter pylori in vitro and in clinical infections [see Indications and Usage (1.2)].

Helicobacter pylori Pretreatment Resistance

Clarithromycin pretreatment resistance (≥2.0 mcg/mL) was 9.5% (91/960) by E-test and 11.3% (12/106) by agar dilution in the dual and triple therapy clinical trials (M93-125, M93-130, M93-131, M95-392, and M95-399).

Amoxicillin pretreatment susceptible isolates (≤0.25 mcg/mL) occurred in 97.8% (936/957) and 98.0% (98/100) of the patients in the dual and triple therapy clinical trials by E-test and agar dilution, respectively. Twenty-one of 957 patients (2.2%) by E-test, and two of 100 patients (2.0%) by agar dilution, had amoxicillin pretreatment MICs of greater than 0.25 mcg/mL. One patient on the 14 day triple therapy regimen had an unconfirmed pretreatment amoxicillin minimum inhibitory concentration (MIC) of greater than 256 mcg/mL by E-test and the patient was eradicated of H. pylori (Table 8).

Table 8. Clarithromycin Susceptibility Test Results and Clinical/Bacteriological Outcomes [Includes only patients with pretreatment clarithromycin susceptibility test results]
Clarithromycin Pretreatment Results |  | Clarithromycin Post-treatment Results
 |  | H. pylori negative - eradicated | H. pylori positive – not eradicated Post-treatment susceptibility results
 |  | H. pylori negative - eradicated | S [Susceptible (S) MIC ≤0.25 mcg/mL, Intermediate (I) MIC 0.5 to 1.0 mcg/mL, Resistant (R) MIC ≥2 mcg/mL] | I | R | No MIC
Triple Therapy 14 Day (lansoprazole 30 mg twice daily/amoxicillin 1 g twice daily/clarithromycin 500 mg twice daily) (M95-399, M93-131, M95-392)
Susceptible | 112 | 105 |  |  |  | 7
Intermediate | 3 | 3
Resistant | 17 | 6 |  |  | 7 | 4
Triple Therapy 10 Day (lansoprazole 30 mg twice daily/amoxicillin 1 g twice daily/clarithromycin 500 mg twice daily) (M95-399)
Susceptible | 42 | 40 | 1 |  | 1
Intermediate
Resistant | 4 | 1 |  |  | 3

Patients not eradicated of H. pylori following lansoprazole/amoxicillin/clarithromycin triple therapy will likely have clarithromycin resistant H. pylori. Therefore, for those patients who fail therapy, clarithromycin susceptibility testing should be done when possible. Patients with clarithromycin resistant H. pylori should not be treated with lansoprazole/amoxicillin/clarithromycin triple therapy or with regimens which include clarithromycin as the sole antimicrobial agent.

Amoxicillin Susceptibility Test Results and Clinical/Bacteriological Outcomes: In the dual and triple therapy clinical trials, 82.6% (195/236) of the patients that had pretreatment amoxicillin susceptible MICs (≤0.25 mcg/mL) were eradicated of H. pylori. Of those with pretreatment amoxicillin MICs of greater than 0.25 mcg/mL, three of six had the H. pylori eradicated. A total of 30% (21/70) of the patients failed lansoprazole 30 mg three times daily/amoxicillin 1 g three times daily dual therapy and a total of 12.8% (22/172) of the patients failed the 10 and 14 day triple therapy regimens. Post-treatment susceptibility results were not obtained on 11 of the patients who failed therapy. Nine of the 11 patients with amoxicillin post-treatment MICs that failed the triple therapy regimen also had clarithromycin resistant H. pylori isolates.

Susceptibility Test for Helicobacter pylori: For susceptibility testing information about Helicobacter pylori, see Microbiology section in prescribing information for clarithromycin and amoxicillin.

13 NONCLINICAL TOXICOLOGY

13.1 Carcinogenesis, Mutagenesis, Impairment of Fertility

In two, 24 month carcinogenicity studies, Sprague-Dawley rats were treated with oral lansoprazole doses of 5 to 150 mg/kg/day, about one to 40 times the exposure on a body surface (mg/m^2) basis of a 50 kg person of average height [1.46 m^2 body surface area (BSA)] given the recommended human dose of 30 mg/day. Lansoprazole produced dose-related gastric enterochromaffin-like (ECL) cell hyperplasia and ECL cell carcinoids in both male and female rats. It also increased the incidence of intestinal metaplasia of the gastric epithelium in both sexes. In male rats, lansoprazole produced a dose-related increase of testicular interstitial cell adenomas. The incidence of these adenomas in rats receiving doses of 15 to 150 mg/kg/day (four to 40 times the recommended human dose based on BSA) exceeded the low background incidence (range = 1.4 to 10%) for this strain of rat.

In a 24 month carcinogenicity study, CD-1 mice were treated with oral lansoprazole doses of 15 to 600 mg/kg/day, two to 80 times the recommended human dose based on BSA. Lansoprazole produced a dose-related increased incidence of gastric ECL cell hyperplasia. It also produced an increased incidence of liver tumors (hepatocellular adenoma plus carcinoma). The tumor incidences in male mice treated with 300 and 600 mg/kg/day (40 to 80 times the recommended human dose based on BSA) and female mice treated with 150 to 600 mg/kg/day (20 to 80 times the recommended human dose based on BSA) exceeded the ranges of background incidences in historical controls for this strain of mice. Lansoprazole treatment produced adenoma of rete testis in male mice receiving 75 to 600 mg/kg/day (10 to 80 times the recommended human dose based on BSA).

A 26 week p53 (+/-) transgenic mouse carcinogenicity study was not positive.

Lansoprazole was positive in the Ames test and the in vitro human lymphocyte chromosomal aberration assay. Lansoprazole was not genotoxic in the ex vivo rat hepatocyte unscheduled DNA synthesis (UDS) test, the in vivo mouse micronucleus test, or the rat bone marrow cell chromosomal aberration test.

Lansoprazole at oral doses up to 150 mg/kg/day (40 times the recommended human dose based on BSA) was found to have no effect on fertility and reproductive performance of male and female rats.

14 CLINICAL STUDIES

14.1 Duodenal Ulcer

In a US multicenter, double-blind, placebo-controlled, dose-response (15, 30, and 60 mg of PREVACID once daily) study of 284 patients with endoscopically documented duodenal ulcer, the percentage of patients healed after two and four weeks was significantly higher with all doses of PREVACID than with placebo. There was no evidence of a greater or earlier response with the two higher doses compared with PREVACID 15 mg. Based on this study and the second study described below, the recommended dose of PREVACID in duodenal ulcer is 15 mg per day (Table 9).

Table 9. Duodenal Ulcer Healing Rates
Week | PREVACID |  |  | Placebo (N=72)
Week | 15 mg daily (N=68) | 30 mg daily (N=74) | 60 mg daily (N=70) | Placebo (N=72)
2 | 42.4% [(p≤0.001) vs placebo.] | 35.6% | 39.1% | 11.3%
4 | 89.4% | 91.7% | 89.9% | 46.1%

PREVACID 15 mg was significantly more effective than placebo in relieving day and nighttime abdominal pain and in decreasing the amount of antacid taken per day.

In a second US multicenter study, also double-blind, placebo-controlled, dose-comparison (15 and 30 mg of PREVACID once daily), and including a comparison with ranitidine, in 280 patients with endoscopically documented duodenal ulcer, the percentage of patients healed after four weeks was significantly higher with both doses of PREVACID than with placebo. There was no evidence of a greater or earlier response with the higher dose of PREVACID. Although the 15 mg dose of PREVACID was superior to ranitidine at four weeks, the lack of significant difference at two weeks and the absence of a difference between 30 mg of PREVACID and ranitidine leaves the comparative effectiveness of the two agents undetermined (Table 10) [see Indications and Usage (1.1)].

Table 10. Duodenal Ulcer Healing Rates
Week | PREVACID |  | Ranitidine | Placebo (N=41)
Week | 15 mg daily (N=80) | 30 mg daily (N=77) | 300 mg h.s. (N=82) | Placebo (N=41)
2 | 35.0% | 44.2% | 30.5% | 34.2%
4 | 92.3% [(p≤0.05) vs placebo and ranitidine.] | 80.3% [(p≤0.05) vs placebo.] | 70.5% | 47.5%

14.2 Eradication of H. pylori to Reduce the Risk of Duodenal Ulcer Recurrence

Randomized, double-blind clinical studies performed in the US in patients with H. pylori and duodenal ulcer disease (defined as an active ulcer or history of an ulcer within one year) evaluated the efficacy of PREVACID in combination with amoxicillin and clarithromycin as triple 14 day therapy or in combination with amoxicillin as dual 14 day therapy for the eradication of H. pylori. Based on the results of these studies, the safety and efficacy of two different eradication regimens were established:

Triple therapy: PREVACID 30 mg twice daily/amoxicillin 1 g twice daily/clarithromycin 500 mg twice daily

Dual therapy: PREVACID 30 mg three times daily/amoxicillin 1 g three times daily

All treatments were for 14 days. H. pylori eradication was defined as two negative tests (culture and histology) at four to six weeks following the end of treatment.

Triple therapy was shown to be more effective than all possible dual therapy combinations. Dual therapy was shown to be more effective than both monotherapies. Eradication of H. pylori has been shown to reduce the risk of duodenal ulcer recurrence.

A randomized, double-blind clinical study performed in the US in patients with H. pylori and duodenal ulcer disease (defined as an active ulcer or history of an ulcer within one year) compared the efficacy of PREVACID triple therapy for 10 and 14 days. This study established that the 10 day triple therapy was equivalent to the 14 day triple therapy in eradicating H. pylori (Tables 11 and 12) [see Indications and Usage (1.2)].

Table 11. H. pylori Eradication Rates – Triple Therapy (PREVACID/amoxicillin/clarithromycin) Percent of Patients Cured [95% Confidence Interval] (Number of patients)
Study | Duration | Triple Therapy Evaluable Analysis [Based on evaluable patients with confirmed duodenal ulcer (active or within one year) and H. pylori infection at baseline defined as at least two of three positive endoscopic tests from CLOtest, histology and/or culture. Patients were included in the analysis if they completed the study. Additionally, if patients dropped out of the study due to an adverse event related to the study drug, they were included in the evaluable analysis as failures of therapy.] | Triple Therapy Intent-to-Treat Analysis [Patients were included in the analysis if they had documented H. pylori infection at baseline as defined above and had a confirmed duodenal ulcer (active or within one year). All dropouts were included as failures of therapy.]
M93-131 | 14 days | 92 [(p<0.05) vs PREVACID/amoxicillin and PREVACID/clarithromycin dual therapy.] [80.0-97.7] (N=48) | 86 [73.3-93.5] (N=55)
M95-392 | 14 days | 86 [(p<0.05) vs clarithromycin/amoxicillin dual therapy.] [75.7-93.6] (N=66) | 83 [72.0-90.8] (N=70)
M95-399 [The 95% confidence interval for the difference in eradication rates, 10 day minus 14 day is (-10.5, 8.1) in the evaluable analysis and (-9.7, 9.1) in the intent-to-treat analysis.] | 14 days | 85 [77.0-91.0] (N=113) | 82 [73.9-88.1] (N=126)
M95-399 [The 95% confidence interval for the difference in eradication rates, 10 day minus 14 day is (-10.5, 8.1) in the evaluable analysis and (-9.7, 9.1) in the intent-to-treat analysis.] | 10 days | 84 [76.0-89.8] (N=123) | 81 [73.9-87.6] (N=135)

Table 12. H. pylori Eradication Rates – 14 Day Dual Therapy (PREVACID/amoxicillin) Percent of Patients Cured [95% Confidence Interval] (Number of patients)
Study | Dual Therapy Evaluable Analysis [Based on evaluable patients with confirmed duodenal ulcer (active or within one year) and H. pylori infection at baseline defined as at least two of three positive endoscopic tests from CLOtest, histology and/or culture. Patients were included in the analysis if they completed the study. Additionally, if patients dropped out of the study due to an adverse event related to the study drug, they were included in the analysis as failures of therapy.] | Dual Therapy Intent-to-Treat Analysis [Patients were included in the analysis if they had documented H. pylori infection at baseline as defined above and had a confirmed duodenal ulcer (active or within one year). All dropouts were included as failures of therapy.]
M93-131 | 77 [(p<0.05) vs PREVACID alone.] [62.5-87.2] (N=51) | 70 [56.8-81.2] (N=60)
M93-125 | 66 [(p<0.05) vs PREVACID alone or amoxicillin alone.] [51.9-77.5] (N=58) | 61 [48.5-72.9] (N=67)

14.3 Maintenance of Healed Duodenal Ulcers

PREVACID has been shown to prevent the recurrence of duodenal ulcers. Two independent, double-blind, multicenter, controlled trials were conducted in patients with endoscopically confirmed healed duodenal ulcers. Patients remained healed significantly longer and the number of recurrences of duodenal ulcers was significantly less in patients treated with PREVACID than in patients treated with placebo over a 12 month period (Table 13) [see Indications and Usage (1.3)].

Table 13. Endoscopic Remission Rates
Trial | Drug | No. of Pts. | Percent in Endoscopic Remission
Trial | Drug | No. of Pts. | 0-3 mo. | 0-6 mo. | 0-12 mo.
#1 | PREVACID 15 mg daily | 86 | 90% [(p≤0.001) vs placebo.] | 87% | 84%
#1 | Placebo | 83 | 49% | 41% | 39%
#2 | PREVACID 30 mg daily | 18 | 94% | 94% | 85%
#2 | PREVACID 15 mg daily | 15 | 87% | 79% | 70%
#2 | Placebo | 15 | 33% | 0% | 0%
%=Life Table Estimate

In trial #2, no significant difference was noted between PREVACID 15 and 30 mg in maintaining remission.

14.4 Gastric Ulcer

In a US multicenter, double-blind, placebo-controlled study of 253 patients with endoscopically documented gastric ulcer, the percentage of patients healed at four and eight weeks was significantly higher with PREVACID 15 and 30 mg once a day than with placebo (Table 14) [see Indications and Usage (1.4)].

Table 14. Gastric Ulcer Healing Rates
Week | PREVACID |  |  | Placebo (N=64)
Week | 15 mg daily (N=65) | 30 mg daily (N=63) | 60 mg daily (N=61) | Placebo (N=64)
4 | 64.6% [(p≤0.05) vs placebo.] | 58.1% | 53.3% | 37.5%
8 | 92.2% | 96.8% | 93.2% | 76.7%

Patients treated with any PREVACID dose reported significantly less day and night abdominal pain along with fewer days of antacid use and fewer antacid tablets used per day than the placebo group.

Independent substantiation of the effectiveness of PREVACID 30 mg was provided by a meta-analysis of published and unpublished data.

14.5 Healing of NSAID-Associated Gastric Ulcer

In two US and Canadian multicenter, double-blind, active-controlled studies in patients with endoscopically confirmed NSAID-associated gastric ulcer who continued their NSAID use, the percentage of patients healed after eight weeks was statistically significantly higher with 30 mg of PREVACID than with the active control. A total of 711 patients were enrolled in the study, and 701 patients were treated. Patients ranged in age from 18 to 88 years (median age 59 years), with 67% female patients and 33% male patients. Race was distributed as follows: 87% Caucasian, 8% Black, 5% Other. There was no statistically significant difference between PREVACID 30 mg daily and the active control on symptom relief (i.e., abdominal pain) (Table 15) [see Indications and Usage (1.5)].

Table 15. NSAID-Associated Gastric Ulcer Healing Rates [Actual observed ulcer(s) healed at time points ±2 days.]
Study #1
 | PREVACID 30 mg daily | Active Control [Dose for healing of gastric ulcer.]
Week 4 | 60% (53/88) [(p≤0.05) vs the active control.] | 28% (23/83)
Week 8 | 79% (62/79) | 55% (41/74)
Study #2
 | PREVACID 30 mg daily | Active Control
Week 4 | 53% (40/75) | 38% (31/82)
Week 8 | 77% (47/61) | 50% (33/66)

14.6 Risk Reduction of NSAID-Associated Gastric Ulcer

In one large US, multicenter, double-blind, placebo- and misoprostol-controlled (misoprostol blinded only to the endoscopist) study in patients who required chronic use of an NSAID and who had a history of an endoscopically documented gastric ulcer, the proportion of patients remaining free from gastric ulcer at four, eight, and 12 weeks was significantly higher with 15 or 30 mg of PREVACID than placebo. A total of 537 patients were enrolled in the study, and 535 patients were treated. Patients ranged in age from 23 to 89 years (median age 60 years), with 65% female patients and 35% male patients. Race was distributed as follows: 90% Caucasian, 6% Black, 4% Other. The 30 mg dose of PREVACID demonstrated no additional benefit in risk reduction of the NSAID-associated gastric ulcer than the 15 mg dose (Table 16) [see Indications and Usage (1.6)].

Table 16. Proportion of Patients Remaining Free of Gastric Ulcers [% = Life Table Estimate]
Week | PREVACID 15 mg daily (N=121) | PREVACID 30 mg daily (N=116) | Misoprostol 200 mcg four times daily (N=106) | Placebo (N=112)
4 | 90% | 92% | 96% | 66%
8 | 86% | 88% | 95% | 60%
12 | 80% | 82% | 93% | 51%
(p<0.001) PREVACID 15 mg daily vs placebo; PREVACID 30 mg daily vs placebo; and misoprostol 200 mcg four times daily vs placebo.
(p<0.05) Misoprostol 200 mcg four times daily vs PREVACID 15 mg daily; and misoprostol 200 mcg four times daily vs PREVACID 30 mg daily.

14.7 Symptomatic Gastroesophageal Reflux Disease (GERD)

Symptomatic GERD: In a US multicenter, double-blind, placebo-controlled study of 214 patients with frequent GERD symptoms, but no esophageal erosions by endoscopy, significantly greater relief of heartburn associated with GERD was observed with the administration of lansoprazole 15 mg once daily up to eight weeks than with placebo. No significant additional benefit from lansoprazole 30 mg once daily was observed.

The intent-to-treat analyses demonstrated significant reduction in frequency and severity of day and night heartburn. Data for frequency and severity for the eight week treatment period are presented in Table 17 and in Figures 1 and 2:

Table 17. Frequency of Heartburn
Variable | Placebo (n=43) | PREVACID 15 mg (n=80) | PREVACID 30 mg (n=86)
Variable | Median
% of Days without Heartburn
Week 1 | 0% | 71% [(p<0.01) vs placebo.] | 46%
Week 4 | 11% | 81% | 76%
Week 8 | 13% | 84% | 82%
% of Nights without Heartburn
Week 1 | 17% | 86% | 57%
Week 4 | 25% | 89% | 73%
Week 8 | 36% | 92% | 80%

Figure 1

Figure 2

In two US, multicenter double-blind, ranitidine-controlled studies of 925 total patients with frequent GERD symptoms, but no esophageal erosions by endoscopy, lansoprazole 15 mg was superior to ranitidine 150 mg (twice daily) in decreasing the frequency and severity of day and night heartburn associated with GERD for the eight week treatment period. No significant additional benefit from lansoprazole 30 mg once daily was observed [see Indications and Usage (1.7)].

14.8 Erosive Esophagitis

In a US, multicenter, double-blind, placebo-controlled study of 269 patients entering with an endoscopic diagnosis of esophagitis with mucosal grading of two or more and grades three and four signifying erosive disease, the percentages of patients with healing are presented in Table 18:

Table 18. Erosive Esophagitis Healing Rates
Week | PREVACID |  |  | Placebo (N=63)
Week | 15 mg daily (N=69) | 30 mg daily (N=65) | 60 mg daily (N=72) | Placebo (N=63)
4 | 67.6% [(p≤0.001) vs placebo.] | 81.3% [(p≤0.05) vs PREVACID 15 mg.] | 80.6% | 32.8%
6 | 87.7% | 95.4% | 94.3% | 52.5%
8 | 90.9% | 95.4% | 94.4% | 52.5%

In this study, all PREVACID groups reported significantly greater relief of heartburn and less day and night abdominal pain along with fewer days of antacid use and fewer antacid tablets taken per day than the placebo group. Although all doses were effective, the earlier healing in the higher two doses suggests 30 mg daily as the recommended dose.

PREVACID was also compared in a US, multicenter, double-blind study to a low dose of ranitidine in 242 patients with erosive reflux esophagitis. PREVACID at a dose of 30 mg was significantly more effective than ranitidine 150 mg twice daily as shown below (Table 19).

Table 19. Erosive Esophagitis Healing Rates
Week | PREVACID 30 mg daily (N=115) | Ranitidine 150 mg twice daily (N=127)
2 | 66.7% [(p≤0.001) vs ranitidine.] | 38.7%
4 | 82.5% | 52.0%
6 | 93.0% | 67.8%
8 | 92.1% | 69.9%

In addition, patients treated with PREVACID reported less day and nighttime heartburn and took less antacid tablets for fewer days than patients taking ranitidine 150 mg twice daily.

Although this study demonstrates effectiveness of PREVACID in healing erosive esophagitis, it does not represent an adequate comparison with ranitidine because the recommended ranitidine dose for esophagitis is 150 mg four times daily, twice the dose used in this study.

In the two trials described and in several smaller studies involving patients with moderate to severe erosive esophagitis, PREVACID produced healing rates similar to those shown above.

In a US, multicenter, double-blind, active-controlled study, 30 mg of PREVACID was compared with ranitidine 150 mg twice daily in 151 patients with erosive reflux esophagitis that was poorly responsive to a minimum of 12 weeks of treatment with at least one H2-receptor antagonist given at the dose indicated for symptom relief or greater, namely, cimetidine 800 mg/day, ranitidine 300 mg/day, famotidine 40 mg/day or nizatidine 300 mg/day. PREVACID 30 mg was more effective than ranitidine 150 mg twice daily in healing reflux esophagitis, and the percentage of patients with healing were as follows. This study does not constitute a comparison of the effectiveness of histamine H2-receptor antagonists with PREVACID, as all patients had demonstrated unresponsiveness to the histamine H2-receptor antagonist mode of treatment. It does indicate, however, that PREVACID may be useful in patients failing on a histamine H2-receptor antagonist (Table 20) [see Indications and Usage (1.7)].

Table 20. Reflux Esophagitis Healing Rates in Patients Poorly Responsive to Histamine H2-Receptor Antagonist Therapy
Week | PREVACID 30 mg daily (N=100) | Ranitidine 150 mg twice daily (N=51)
4 | 74.7% [(p≤0.001) vs ranitidine.] | 42.6%
8 | 83.7% | 32.0%

14.9 Maintenance of Healing of Erosive Esophagitis

Two independent, double-blind, multicenter, controlled trials were conducted in patients with endoscopically confirmed healed esophagitis. Patients remained in remission significantly longer and the number of recurrences of erosive esophagitis was significantly less in patients treated with PREVACID than in patients treated with placebo over a 12 month period (Table 21).

Table 21. Endoscopic Remission Rates
 |  |  | Percent in Endoscopic Remission
Trial | Drug | No. of Pts. | 0-3 mo. | 0-6 mo. | 0-12 mo.
#1 | PREVACID 15 mg daily | 59 | 83% [(p≤0.001) vs placebo.] | 81% | 79%
#1 | PREVACID 30 mg daily | 56 | 93% | 93% | 90%
#1 | Placebo | 55 | 31% | 27% | 24%
#2 | PREVACID 15 mg daily | 50 | 74% | 72% | 67%
#2 | PREVACID 30 mg daily | 49 | 75% | 72% | 55%
#2 | Placebo | 47 | 16% | 13% | 13%
%=Life Table Estimate

Regardless of initial grade of erosive esophagitis, PREVACID 15 and 30 mg were similar in maintaining remission.

In a US, randomized, double-blind study, PREVACID 15 mg daily (n=100) was compared with ranitidine 150 mg twice daily (n=106), at the recommended dosage, in patients with endoscopically-proven healed erosive esophagitis over a 12 month period. Treatment with PREVACID resulted in patients remaining healed (Grade 0 lesions) of erosive esophagitis for significantly longer periods of time than those treated with ranitidine (p<0.001). In addition, PREVACID was significantly more effective than ranitidine in providing complete relief of both daytime and nighttime heartburn. Patients treated with PREVACID remained asymptomatic for a significantly longer period of time than patients treated with ranitidine [see Indications and Usage (1.9)].

14.10 Pathological Hypersecretory Conditions Including Zollinger-Ellison Syndrome

In open studies of 57 patients with pathological hypersecretory conditions, such as Zollinger-Ellison syndrome (ZES) with or without multiple endocrine adenomas, PREVACID significantly inhibited gastric acid secretion and controlled associated symptoms of diarrhea, anorexia and pain. Doses ranging from 15 mg every other day to 180 mg per day maintained basal acid secretion below 10 mEq/hr in patients without prior gastric surgery and below 5 mEq/hr in patients with prior gastric surgery.

Initial doses were titrated to the individual patient need, and adjustments were necessary with time in some patients [see Dosage and Administration (2.1)]. PREVACID was well-tolerated at these high-dose levels for prolonged periods (greater than four years in some patients). In most ZES patients, serum gastrin levels were not modified by PREVACID. However, in some patients, serum gastrin increased to levels greater than those present prior to initiation of lansoprazole therapy [see Indications and Usage (1.10)].

16 HOW SUPPLIED/STORAGE AND HANDLING

PREVACID 15 mg strength is not currently marketed by Takeda Pharmaceuticals America, Inc.

PREVACID 30 mg delayed-release capsules are opaque, pink and black with "TAP" and "PREVACID 30" imprinted on the capsules. They are available as follows:

NDC Number | Size
64764-046-13 | Bottles of 100: 30 mg capsules

PREVACID SoluTab delayed-release orally disintegrating tablets, 15 mg, are white to yellowish white, round uncoated tablets containing orange to dark brown speckles, with "15" debossed on one side of the tablet. The 30 mg are white to yellowish white, round uncoated tablets containing orange to dark brown speckles, with "30" debossed on one side of the tablet. The tablets are available as follows:

NDC Number | Size
64764-543-11 | Unit dose packages of 100: 15 mg tablets
64764-544-11 | Unit dose packages of 100: 30 mg tablets

STORAGE AND HANDLING

Store at 25°C (77°F); excursions permitted to 15 to 30°C (59 to 86°F) [see USP Controlled Room Temperature].

17 PATIENT COUNSELING INFORMATION

Advise the patient to read the FDA-approved patient labeling (Medication Guide and Instructions for Use).

Advise patients to:

Acute Tubulointerstitial Nephritis

To call their healthcare provider if they experience signs and/or symptoms associated with acute tubulointerstitial nephritis [see Warnings and Precautions (5.2)].

Clostridium difficile-Associated Diarrhea

To immediately call their healthcare provider if they experience diarrhea that does not improve [see Warnings and Precautions (5.3)].

Bone Fracture

To report any fractures, especially of the hip, wrist or spine, to their healthcare provider [see Warnings and Precautions (5.4)].

Severe Cutaneous Adverse Reactions

To discontinue PREVACID or PREVACID SoluTab and immediately call their healthcare provider for further evaluation [see Warnings and Precautions (5.5)].

Cutaneous and Systemic Lupus Erythematosus

To immediately call their healthcare provider for any new or worsening of symptoms associated with cutaneous or systemic lupus erythematosus [see Warnings and Precautions (5.6)].

Cyanocobalamin (Vitamin B12) Deficiency

To report any clinical symptoms that may be associated with cyanocobalamin deficiency to their healthcare provider, if they have been receiving PREVACID or PREVACID SoluTab for longer than three years [see Warnings and Precautions (5.7)].

Hypomagnesemia and Mineral Metabolism

To report any clinical symptoms that may be associated with hypomagnesemia, hypocalcemia, and/or hypokalemia to their healthcare provider, if they have been receiving PREVACID or PREVACID SoluTab for at least three months [see Warnings and Precautions (5.8)].

Drug Interactions

Advise patients to report to their healthcare provider if they are taking rilpivirine-containing products [see Contraindications (4)] or high-dose methotrexate [see Warnings and Precautions (5.10)].

Pregnancy

Advise a pregnant woman of the potential risk to a fetus. Advise females of reproductive potential to inform their healthcare provider of a known or suspected pregnancy [see Use in Specific Populations (8.1)].

Administration

- Missed doses: If a dose is missed, administer as soon as possible. However, if the next scheduled dose is due, do not take the missed dose, and take the next dose on time. Do not take two doses at one time to make up for a missed dose.
  - PREVACID or PREVACID SoluTab should be taken before eating.
  - Do not crush or chew PREVACID capsule or PREVACID SoluTab.
  - Take PREVACID or PREVACID SoluTab at least 30 minutes prior to sucralfate.
  - Phenylketonurics: Contains Phenylalanine 2.5 mg per 15 mg PREVACID SoluTab Tablet and 5.1 mg per 30 mg PREVACID SoluTab Tablet.
  PREVACID Capsules
  - Swallow whole; do not chew.
  - For patients who have difficulty swallowing capsules:
    - PREVACID capsules can be opened and sprinkled on applesauce, ENSURE pudding, cottage cheese, yogurt or strained pears
    - PREVACID capsules may also be emptied into a small volume of either apple juice, orange juice or tomato juice
    - Alternatively, PREVACID capsules can be administered with apple juice via nasogastric tube
    - See the Instructions for Use for a description of all preparation and administration instructions
  PREVACID SoluTab
  - Do not break or cut.
  - Place the tablet on the tongue; allow it to disintegrate, with or without water, until the particles can be swallowed. Do not chew the particles.
  - The tablet typically disintegrates in less than one minute.
  - Alternatively, for children or other patients who have difficulty swallowing tablets, PREVACID SoluTab can be administered with water via oral syringe or NG tube, as described in the Instructions for Use.

MEDICATION GUIDE
PREVACID (prev-a-sid)
(lansoprazole) delayed-release capsules, for oral use
and
PREVACID SoluTab (prev-a-sid sol-u-tab)
(lansoprazole) delayed-release orally disintegrating tablets

What is the most important information that I should know about PREVACID and PREVACID SoluTab?

You should take PREVACID and PREVACID SoluTab exactly as prescribed, at the lowest dose possible and for the shortest time needed.

PREVACID and PREVACID SoluTab may help your acid-related symptoms, but you could still have serious stomach problems. Talk with your doctor.

PREVACID and PREVACID SoluTab can cause serious side effects, including:

- A type of kidney problem (acute tubulointerstitial nephritis). Some people who take proton pump inhibitor (PPI) medicines, including PREVACID and PREVACID SoluTab, may develop a kidney problem called acute tubulointerstitial nephritis that can happen at any time during treatment with PPI medicines including PREVACID and PREVACID SoluTab. Call your doctor right away if you have a decrease in the amount that you urinate or if you have blood in your urine.
- Diarrhea caused by an infection (Clostridium difficile) in your intestines. Call your doctor right away if you have watery stools or stomach pain that does not go away. You may or may not have a fever.
- Bone fractures (hip, wrist, or spine). Bone fractures in the hip, wrist, or spine may happen in people who take multiple daily doses of PPI medicines and for a long period of time (a year or longer). Tell your doctor if you have a bone fracture, especially in the hip, wrist, or spine.
- Certain types of lupus erythematosus. Lupus erythematosus is an autoimmune disorder (the body's immune cells attack other cells or organs in the body). Some people who take PPI medicines, including PREVACID and PREVACID SoluTab, may develop certain types of lupus erythematosus or have worsening of the lupus they already have. Call your doctor right away if you have new or worsening joint pain or a rash on your cheeks or arms that gets worse in the sun.

Talk to your doctor about your risk of these serious side effects.

PREVACID and PREVACID SoluTab can have other serious side effects. See "What are the possible side effects of PREVACID and PREVACID SoluTab?".

What are PREVACID and PREVACID SoluTab?

A prescription medicine called a proton pump inhibitor (PPI) used to reduce the amount of acid in your stomach.

In adults, PREVACID and PREVACID SoluTab are used for:

- 4 weeks for the healing and symptom relief of duodenal ulcers.
- 10 to 14 days with certain antibiotics to treat an infection caused by bacteria called H. pylori.
- maintaining healing of duodenal ulcers. PREVACID has not been studied beyond 12 months for this purpose.
- up to 8 weeks for the healing and symptom relief of stomach ulcers.
- up to 8 weeks for the healing of stomach ulcers in people taking pain medicines called nonsteroidal anti-inflammatory drugs (NSAIDs). PREVACID has not been studied beyond 8 weeks for this purpose.
- reducing the risk of stomach ulcers in people who are at risk of developing stomach ulcers with NSAIDs. PREVACID has not been studied beyond 12 weeks for this purpose.
- up to 8 weeks to treat heartburn and other symptoms that happen with gastroesophageal reflux disease (GERD).
  GERD happens when acid in your stomach backs up into the tube (esophagus) that connects your mouth to your stomach. This may cause a burning feeling in your chest or throat, sour taste or burping.
- up to 8 weeks for the healing and symptom relief of acid-related damage to the lining of the esophagus (called erosive esophagitis or EE). Your doctor may prescribe another 8 to 16 weeks of PREVACID or PREVACID SoluTab for patients whose EE does not improve or whose symptoms return.
- maintaining healing of EE. PREVACID has not been studied beyond 12 months for this purpose.
- the long-term treatment of conditions where your stomach makes too much acid. This includes a rare condition called Zollinger-Ellison syndrome.

Children:

Give PREVACID and PREVACID SoluTab exactly as prescribed by your child's doctor. Do not increase the dose of PREVACID and PREVACID SoluTab or give your child PREVACID and PREVACID SoluTab longer than the amount of time your doctor tells you to.

In children 1 to 11 years of age, PREVACID and PREVACID SoluTab are used for:

- up to 12 weeks to treat heartburn and other symptoms that can happen with GERD.
- up to 12 weeks for the healing and symptom relief of EE.

In children 12 to 17 years of age, PREVACID and PREVACID SoluTab are used for:

- up to 8 weeks to treat heartburn and other symptoms that can happen with GERD.
- up to 8 weeks for the healing and symptom relief of EE.

PREVACID and PREVACID SoluTab are not recommended for treating the symptoms of GERD in children less than 1 year of age and may harm them.

Do not take PREVACID or PREVACID SoluTab if you are:

- allergic to lansoprazole, any other PPI medicine, or any of the ingredients in PREVACID or PREVACID SoluTab. See the end of this Medication Guide for a complete list of ingredients in PREVACID and PREVACID SoluTab.
- taking a medicine that contains rilpivirine (EDURANT, COMPLERA, ODEFSEY, JULUCA) used to treat HIV-1 (Human Immunodeficiency Virus).

Before you take PREVACID or PREVACID SoluTab, tell your doctor about all of your medical conditions, including if you:

- have low magnesium, calcium, potassium or sodium levels in your blood or you are taking a diuretic.
- have liver problems.
- have phenylketonuria. PREVACID SoluTab contains aspartame.
- are pregnant, think you may be pregnant or plan to become pregnant. PREVACID or PREVACID SoluTab may harm your unborn baby. Talk to your doctor about the possible risks to an unborn baby if PREVACID or PREVACID SoluTab is taken during pregnancy.
- are breastfeeding or plan to breastfeed. It is not known if PREVACID or PREVACID SoluTab passes into your breast milk. Talk to your doctor about the best way to feed your baby if you take PREVACID or PREVACID SoluTab.

Tell your doctor about all the medicines you take, including prescription and over-the-counter medicines, vitamins, and herbal supplements. Especially tell your doctor if you take methotrexate (OTREXUP, RASUVO, TREXALL, REDITREX, XATMEP).

How should I take PREVACID and PREVACID SoluTab?

- Take PREVACID or PREVACID SoluTab exactly as prescribed by your doctor.
- Do not change your dose or stop taking PREVACID or PREVACID SoluTab without talking to your doctor.
- Take PREVACID or PREVACID SoluTab before meals.
  PREVACID capsules:
  - Swallow PREVACID capsules whole.
  - Do not crush or chew PREVACID capsules.
  - If you have trouble swallowing a whole capsule, you can open the capsule and take the contents with certain foods or juices. See the "Instructions for Use" at the end of this Medication Guide for instructions on how to take PREVACID capsules with certain foods or juices.
  - See the "Instructions for Use" at the end of this Medication Guide for instructions on how to mix and give PREVACID capsules through a nasogastric tube (NG tube).
  PREVACID SoluTab:
  - PREVACID SoluTab is a tablet that melts in your mouth with or without water.
  - Do not break, cut, crush or chew the tablets.
  - See the "Instructions for Use" at the end of this Medication Guide for instructions on how to mix and give PREVACID SoluTab through a syringe and NG tube.

- If you miss a dose of PREVACID or PREVACID SoluTab, take it as soon as you remember. If it is almost time for your next dose, do not take the missed dose. Take your next dose at your regular time. Do not take 2 doses at the same time.
- If you take too much PREVACID or PREVACID SoluTab, call your doctor or your poison control center at 1-800-222-1222 right away or go to the nearest hospital emergency room.

What are the possible side effects of PREVACID and PREVACID SoluTab?

PREVACID and PREVACID SoluTab can cause serious side effects, including:

- See "What is the most important information that I should know about PREVACID and PREVACID SoluTab?".
- Low vitamin B12 levels in the body can happen in people who have taken PREVACID or PREVACID SoluTab for a long time (more than 3 years). Tell your doctor if you have symptoms of low vitamin B12 levels, including shortness of breath, lightheadedness, irregular heartbeat, muscle weakness, pale skin, feeling tired, mood changes, and tingling or numbness in the arms and legs.
- Stomach growths (fundic gland polyps). People who take PPI medicines for a long time have an increased risk of developing a certain type of stomach growth called fundic gland polyps, especially after taking PPI medicines for more than 1 year.
- Low magnesium levels in the body can happen in people who have taken PREVACID for at least 3 months. Tell your doctor right away if you have symptoms of low magnesium levels, including seizures, dizziness, irregular heartbeat, jitteriness, muscle aches or weakness, and spasms of hands, feet or voice.
- Severe skin reactions. PREVACID can cause rare but severe skin reactions that may affect any part of your body. These serious skin reactions may need to be treated in a hospital and may be life threatening:
  - Skin rash which may have blistering, peeling or bleeding on any part of your skin (including your lips, eyes, mouth, nose, genitals, hands or feet).
  - You may also have fever, chills, body aches, shortness of breath, or enlarged lymph nodes.
  Stop taking PREVACID and call your doctor right away. These symptoms may be the first sign of a severe skin reaction.

The most common side effects of PREVACID and PREVACID SoluTab include: diarrhea, stomach-area (abdomen) pain, nausea and constipation.

These are not all the possible side effects of PREVACID and PREVACID SoluTab.

Call your doctor for medical advice about side effects.

You may report side effects to FDA at 1-800-FDA-1088.

How should I store PREVACID and PREVACID SoluTab?

Store PREVACID at room temperature between 68°F to 77°F (20°C to 25°C).

Keep PREVACID and PREVACID SoluTab and all medicines out of the reach of children.

General information about the safe and effective use of PREVACID and PREVACID SoluTab.

Medicines are sometimes prescribed for purposes other than those listed in a Medication Guide. Do not use PREVACID or PREVACID SoluTab for conditions for which it was not prescribed. Do not give PREVACID or PREVACID SoluTab to other people, even if they have the same symptoms that you have. It may harm them. You can ask your doctor or pharmacist for information about PREVACID and PREVACID SoluTab that is written for health professionals.

What are the ingredients in PREVACID and PREVACID SoluTab?

Active ingredient: lansoprazole.

Inactive ingredients in PREVACID capsules: sugar sphere, sucrose, methacrylic acid copolymer, low substituted hydroxypropyl cellulose, starch, magnesium carbonate, talc, polyethylene glycol, titanium dioxide, polysorbate 80, hydroxypropyl cellulose, colloidal silicon dioxide, D&C Red No. 28, FD&C Blue No. 1, and FD&C Red No. 40.

Inactive ingredients in PREVACID SoluTab: mannitol, methacrylic acid, hydroxypropyl cellulose, lactose monohydrate-microcrystalline cellulose sphere, triethyl citrate, crospovidone, polyacrylate, magnesium carbonate, aspartame, glyceryl monostearate, hypromellose, magnesium stearate, citric acid, titanium dioxide, talc, artificial strawberry flavor, polyethylene glycol, polysorbate 80 and ferric oxide.

PREVACID SoluTab contains 2.5 mg of phenylalanine in each 15 mg tablet and 5.1 mg of phenylalanine in each 30 mg tablet.

Distributed by: Takeda Pharmaceuticals America, Inc., Cambridge, MA 02142

PREVACID is a trademark registered in the U.S. Patent and Trademark Office and SoluTab is a trademark of Takeda Pharmaceuticals U.S.A., Inc. and used under license by Takeda Pharmaceuticals America, Inc.
All other trademark names are the property of their respective owners.
©2025 Takeda Pharmaceuticals America, Inc. All rights reserved.

For more information go to www.PREVACID.com or call 1-877- TAKEDA-7 (1-877- 825-3327).

This Medication Guide has been approved by the U.S. Food and Drug Administration.

Revised: 3/2025

INSTRUCTIONS FOR USE PREVACID (prev-a-sid) (lansoprazole) delayed-release capsules, for oral use and PREVACID SoluTab (prev-a-sid sol-u-tab) (lansoprazole) delayed-release orally disintegrating tablets

Important:

- Take PREVACID or PREVACID SoluTab before meals.
- Do not crush or chew PREVACID capsules or PREVACID SoluTab.
- PREVACID or PREVACID SoluTab should only be used with the foods and juices listed below.

PREVACID delayed-release capsules (PREVACID capsules)

Taking PREVACID capsules with certain foods:

You can only use applesauce, ENSURE pudding, cottage cheese, yogurt or strained pears.

1. Open the capsule.
2. Sprinkle the granules on 1 tablespoon of applesauce, ENSURE pudding, cottage cheese, yogurt or strained pears.
3. Swallow right away.

Taking PREVACID capsules with certain juices:

You can only use apple juice, orange juice or tomato juice.

1. Open the capsule.
2. Sprinkle the granules into 60 mL (about ¼ cup) of apple juice, orange juice or tomato juice.
3. Stir.
4. Swallow right away.
5. To make sure that the entire dose is taken, add 1/2 cup or more of juice to the glass, stir and swallow right away.

Giving PREVACID capsules through a nasogastric tube (NG tube) size 16 French or larger:

You can only use apple juice.

1. Place 40 mL of apple juice into a clean container.
2. Open the capsule and empty the granules into the container of apple juice.
3. Use a catheter-tip syringe to draw up the apple juice and granule mixture.
4. Gently mix the catheter-tip syringe to keep the granules from settling.
5. Attach the catheter-tip syringe to the NG tube.
6. Give the mixture right away through the NG tube that goes into the stomach. Do not save the apple juice and granule mixture for later use.
7. Refill the catheter-tip syringe with 40 mL of apple juice and mix gently. Flush the NG tube with apple juice.

PREVACID SoluTab Delayed-Release Orally Disintegrating Tablets (PREVACID SoluTab)

1. Do not chew, crush, cut or break the tablets.
2. Put the tablet on the tongue and let it dissolve, with or without water.
3. Swallow after the tablet dissolves.
4. The tablet usually dissolves in less than 1 minute.

For patients who have trouble swallowing tablets, PREVACID SoluTab can be given as follows:

Giving PREVACID SoluTab with water using an oral syringe:

1. Put a 15 mg tablet in an oral syringe and draw up 4 mL of water into the oral syringe, or put a 30 mg tablet in an oral syringe and draw up 10 mL of water into the oral syringe.
2. Gently shake the oral syringe to mix the tablet and the water.
3. After the tablet is mixed in the water, place the tip of the oral syringe in the mouth. Give the medicine within 15 minutes of mixing. Do not save the tablet and water mixture for later use.
4. Refill the oral syringe with about 2 mL of water for the 15 mg tablet or 5 mL of water for the 30 mg tablet, and shake gently. Place the tip of the oral syringe in the mouth and give the medicine that is left in the syringe.

Giving PREVACID SoluTab with water through a nasogastric tube (NG tube) size 8 French or larger:

1. Put a 15 mg tablet in a catheter-tip syringe and draw up 4 mL of water, or put a 30 mg tablet in a catheter-tip syringe and draw up 10 mL of water.
2. Gently shake the catheter-tip syringe to mix the tablet and the water.
3. Connect the catheter-tip syringe to the NG tube.
4. Give the mixture right away through the NG tube that goes into the stomach. Give the medicine within 15 minutes of mixing. Do not save the granule and water mixture for later use.
5. Refill the catheter-tip syringe with about 5 mL of water and shake gently. Flush the NG tube with the water.

How should I store PREVACID and PREVACID SoluTab?

- Store PREVACID capsules and PREVACID SoluTab at room temperature between 68°F to 77°F (20°C to 25°C).

Keep PREVACID and PREVACID SoluTab and all medicines out of the reach of children.

This Instruction for Use has been approved by the U.S. Food and Drug Administration.

Distributed by:
Takeda Pharmaceuticals America, Inc.
Cambridge, MA 02142
Revised: March 2025

PREVACID is a trademark registered in the U.S. Patent and Trademark Office and SoluTab is a trademark of Takeda Pharmaceuticals U.S.A., Inc. and used under license by Takeda Pharmaceuticals America, Inc.

All other trademark names are the property of their respective owners.

©2025 Takeda Pharmaceuticals America, Inc. All rights reserved.

PRV012 R57

PRINCIPAL DISPLAY PANEL - 30 mg Capsule Bottle Label

NDC 64764-046-13
100 Capsules

PREVACID®
LANSOPRAZOLE
DELAYED-RELEASE CAPSULES

30 mg

Dispense the accompanying
Medication Guide to each patient.

Takeda

Rx only

PRINCIPAL DISPLAY PANEL - 15 mg Tablet Blister Pack Carton

NDC 64764-543-11

PREVACID® SoluTabTM
LANSOPRAZOLE
Delayed-Release Orally Disintegrating Tablets

15
mg

Rx only

Takeda

Dispense the enclosed
Medication Guide to each patient.

100 Tablets
Contains: 10 Packs of 10 Tablets Each

PRINCIPAL DISPLAY PANEL - 30 mg Tablet Blister Pack Carton

NDC 64764-544-11

PREVACID® SoluTabTM
LANSOPRAZOLE
Delayed-Release Orally Disintegrating Tablets

30
mg

Rx only

Takeda

Dispense the enclosed
Medication Guide to each patient.

100 Tablets
Contains: 10 Packs of 10 Tablets Each